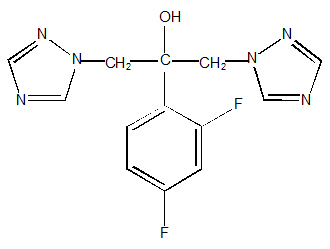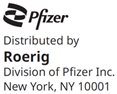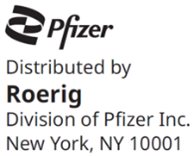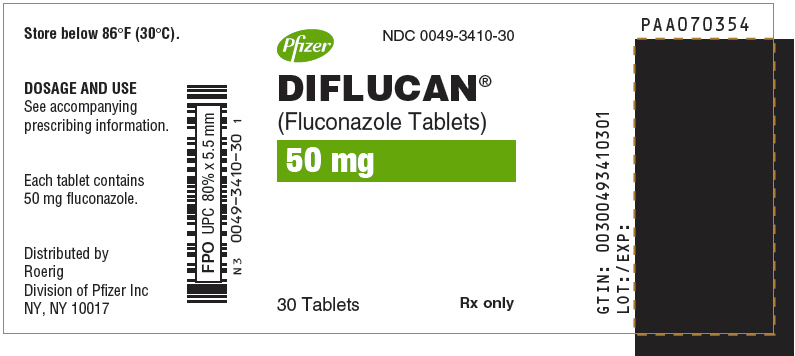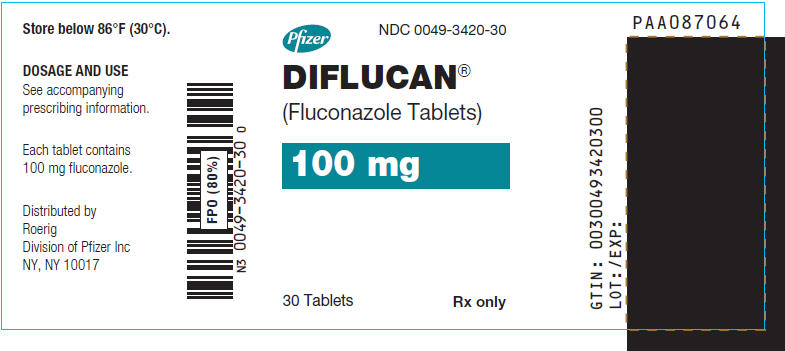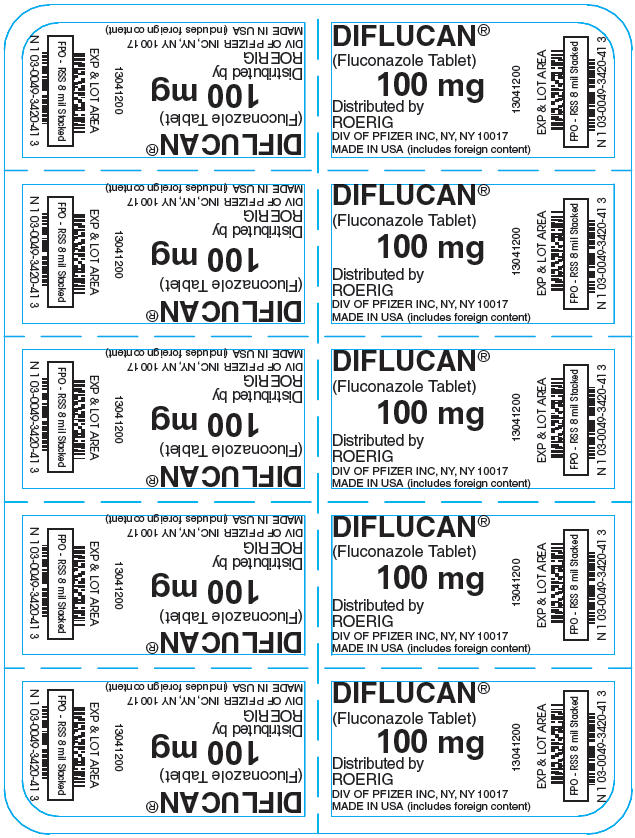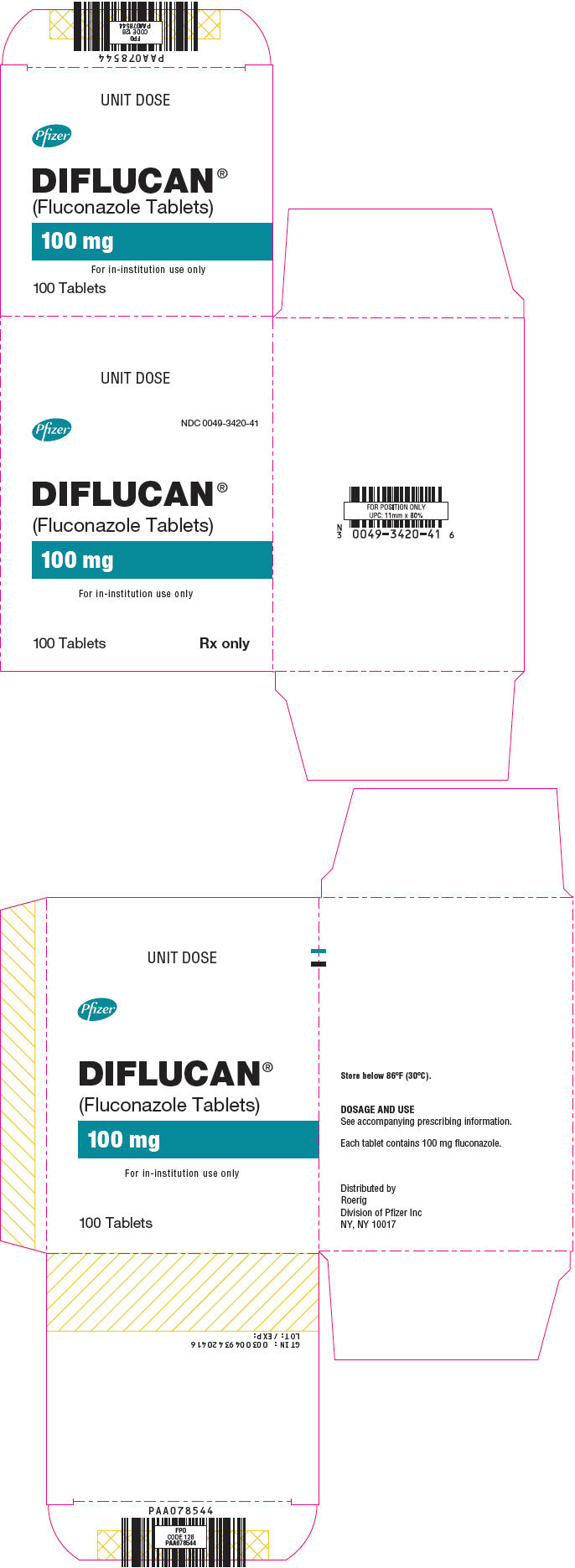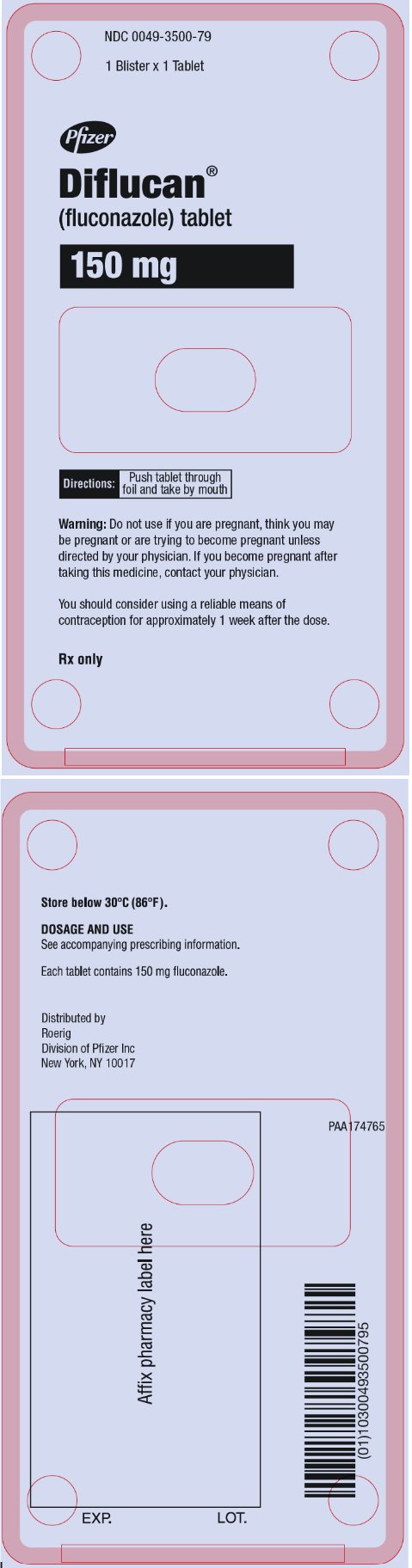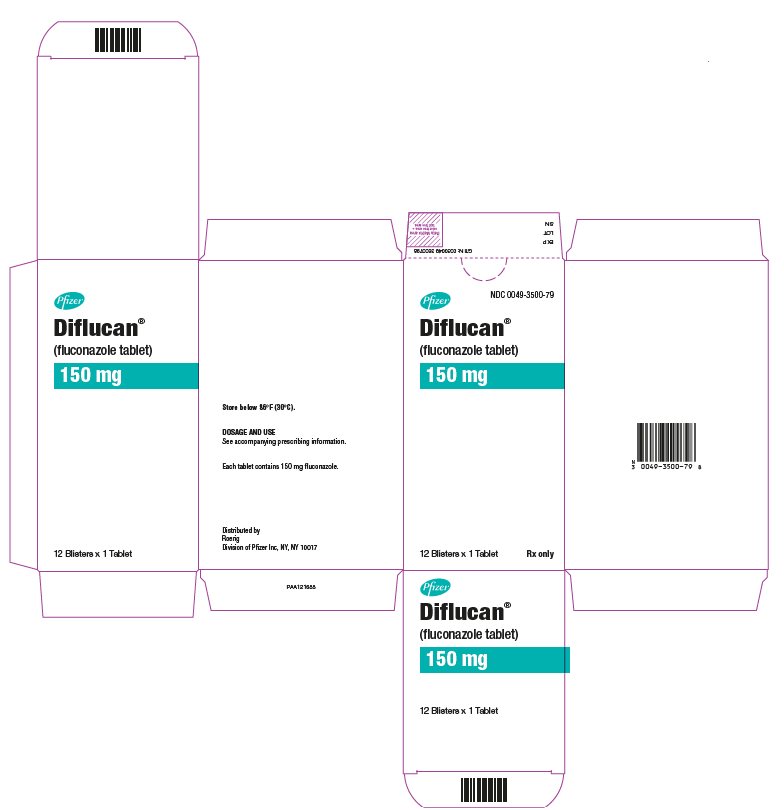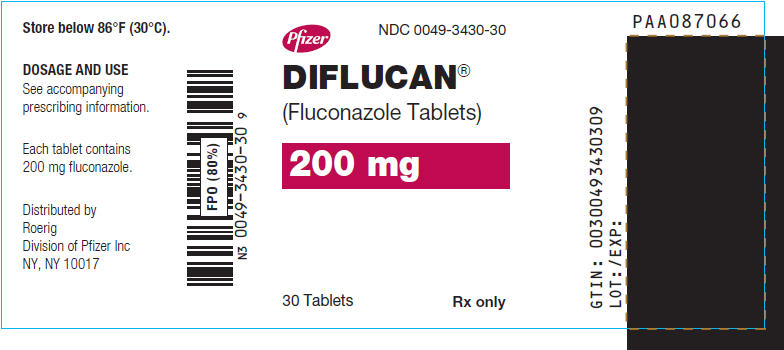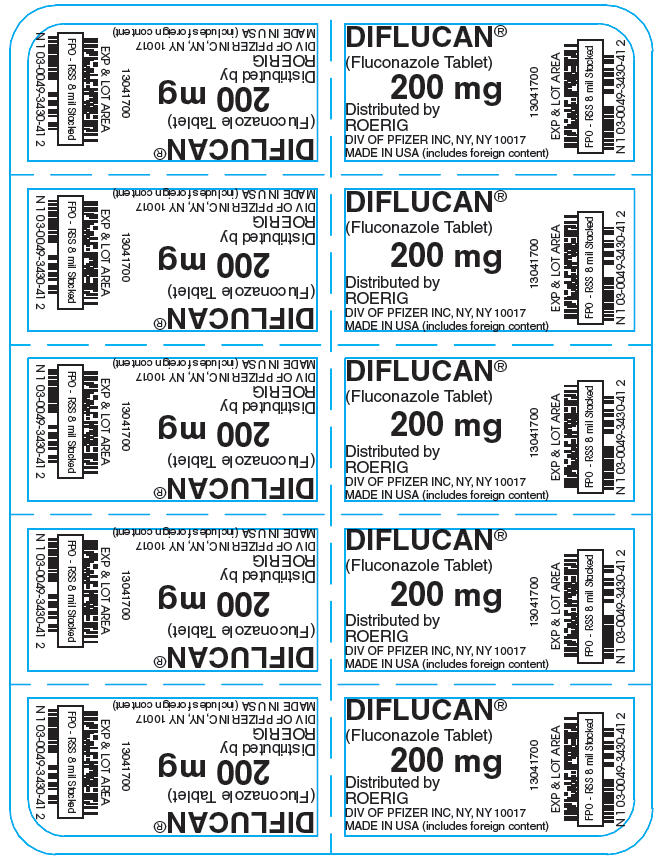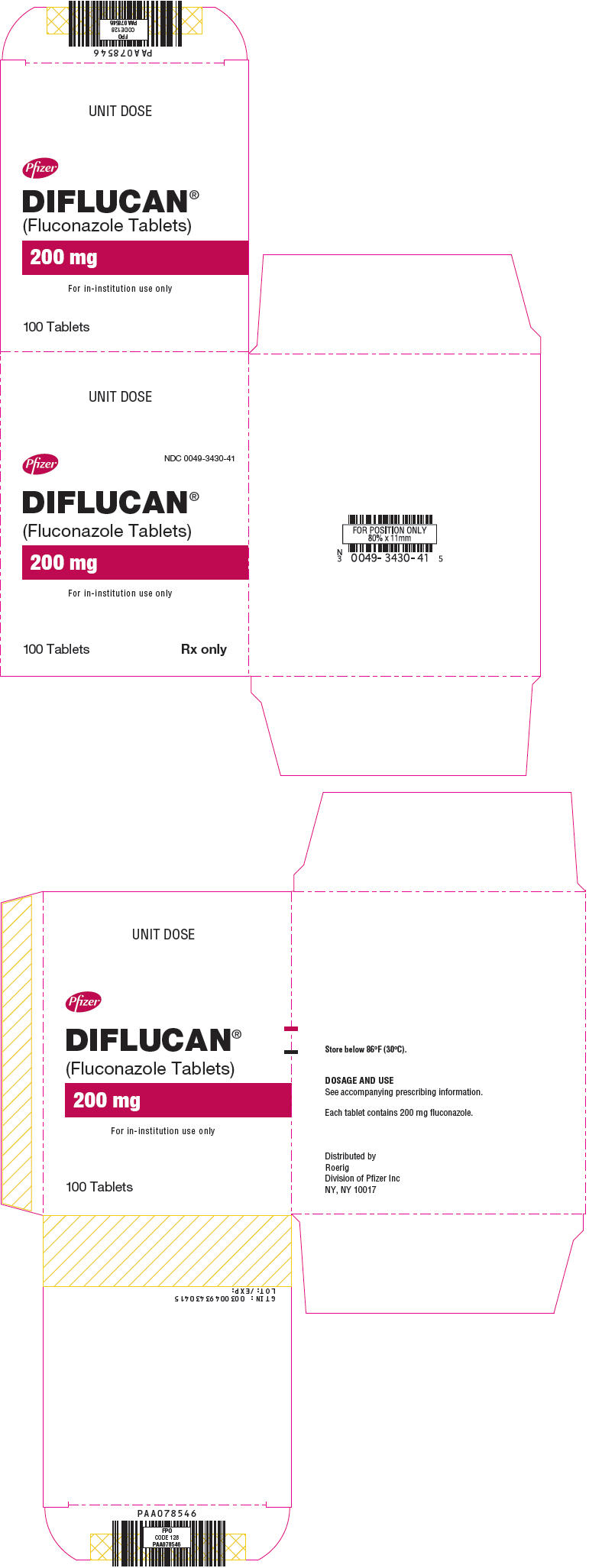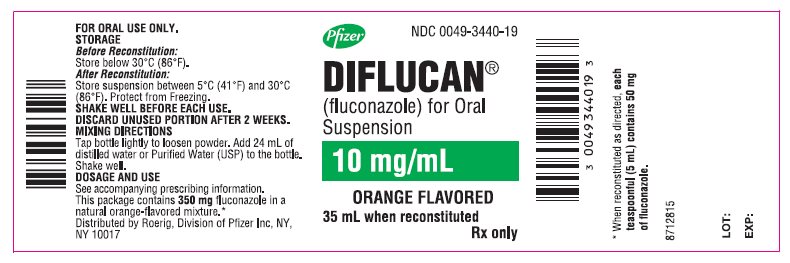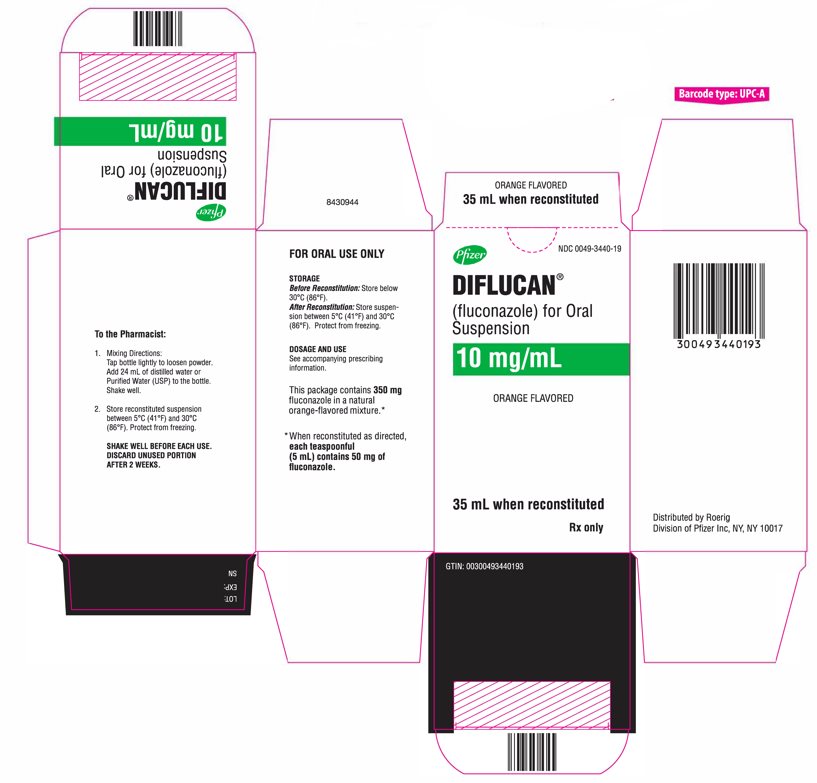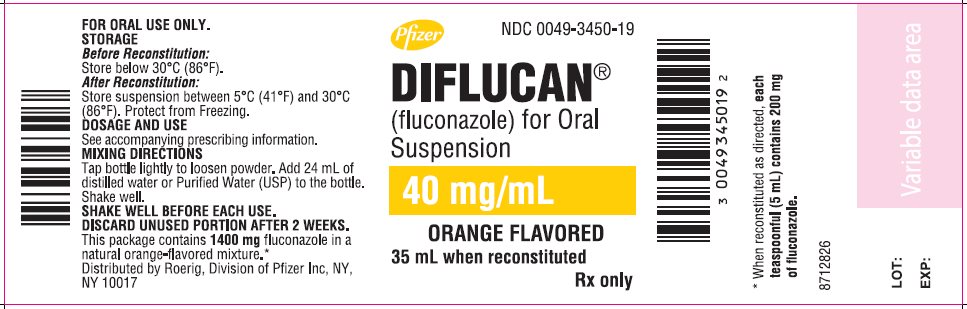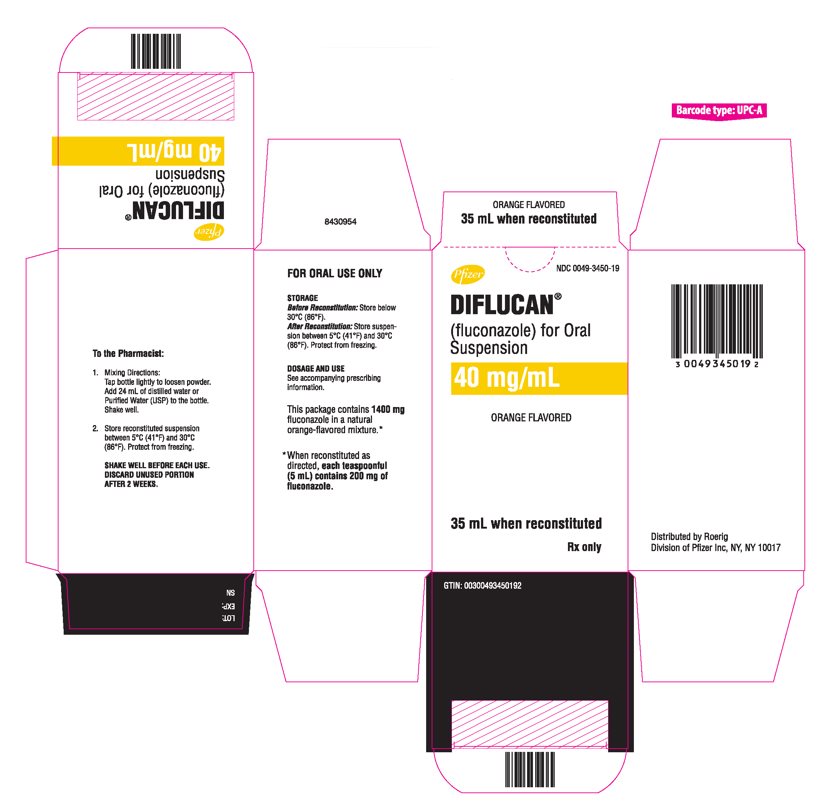 DRUG LABEL: Diflucan
NDC: 0049-3410 | Form: TABLET
Manufacturer: Roerig
Category: prescription | Type: HUMAN PRESCRIPTION DRUG LABEL
Date: 20251010

ACTIVE INGREDIENTS: FLUCONAZOLE 50 mg/1 1
INACTIVE INGREDIENTS: MICROCRYSTALLINE CELLULOSE; ANHYDROUS DIBASIC CALCIUM PHOSPHATE; CROSCARMELLOSE SODIUM; FD&C RED NO. 40; ALUMINUM OXIDE; MAGNESIUM STEARATE; POVIDONE, UNSPECIFIED

DIFLUCAN®
(Fluconazole Tablets)
(Fluconazole for Oral Suspension)

DESCRIPTION

DIFLUCAN® (fluconazole), the first of a new subclass of synthetic triazole antifungal agents, is available as tablets for oral administration, as a powder for oral suspension.

Fluconazole is designated chemically as 2,4-difluoro-α,α^1-bis(1H-1,2,4-triazol-1-ylmethyl) benzyl alcohol with an empirical formula of C13H12F2N6O and molecular weight of 306.3. The structural formula is:

Fluconazole is a white crystalline solid which is slightly soluble in water and saline.

DIFLUCAN Tablets contain 50 mg, 100 mg, 150 mg, or 200 mg of fluconazole and the following inactive ingredients: microcrystalline cellulose, dibasic calcium phosphate anhydrous, povidone, croscarmellose sodium, FD&C Red No. 40 aluminum lake dye, and magnesium stearate.

DIFLUCAN for Oral Suspension contains 350 mg or 1400 mg of fluconazole and the following inactive ingredients: sucrose, sodium citrate dihydrate, citric acid anhydrous, sodium benzoate, titanium dioxide, colloidal silicon dioxide, xanthan gum, and natural orange flavor. After reconstitution with 24 mL of distilled water or Purified Water (USP), each mL of reconstituted suspension contains 10 mg or 40 mg of fluconazole.

CLINICAL PHARMACOLOGY

Pharmacokinetics and Metabolism

The pharmacokinetic properties (PK) of fluconazole are similar following administration by the intravenous or oral routes. In normal volunteers, the bioavailability of orally administered fluconazole is over 90% compared with intravenous administration. Bioequivalence was established between the 100 mg tablet and both suspension strengths when administered as a single 200 mg dose.

Peak plasma concentrations (Cmax) in fasted normal volunteers occur between 1 and 2 hours with a terminal plasma elimination half-life of approximately 30 hours (range: 20 to 50 hours) after oral administration.

In fasted normal volunteers, administration of a single oral 400 mg dose of DIFLUCAN (fluconazole) leads to a mean Cmax of 6.72 mcg/mL (range: 4.12 to 8.08 mcg/mL) and after single or multiple oral doses of 50 to 400 mg, fluconazole plasma concentrations and area under the plasma concentration time curve (AUC) are dose proportional (Table 1).

The Cmax and AUC data from a food-effect study involving administration of DIFLUCAN (fluconazole) tablets to healthy volunteers under fasting conditions and with a high-fat meal indicated that exposure to the drug is not affected by food. Therefore, DIFLUCAN may be taken without regard to meals. (See DOSAGE AND ADMINISTRATION.)

Table 1: Mean Pharmacokinetic Parameters of Fluconazole in Adult Healthy Volunteers Following the Administration of DIFLUCAN

Dose regimen | Cmax (mcg/mL) | AUC0-24 (mcg*h/mL) | Half-life (hours)
50 mg oral (once daily x 7 days) | 2.21 | 37.6 | 26.6
100 mg oral (once daily x 7 days) | 4.81 | 82.5 | 27.7
150 mg single oral | 2.70 | 137* | 34.1
200 mg oral (once daily x 14 days) | 10.12 | 169.5 | 31
300 mg oral (once daily x 14 days) | 15.98 | 299.4 | 34
400 mg oral (once daily x 14 days) | 18.89 | 349.9 | 31

*AUC0-inf. Cmax= peak plasma concentrations, AUC =area under the plasma concentration time curve.

Steady-state concentrations are reached within 5 to 10 days following oral doses of 50 to 400 mg given once daily. Administration of a loading dose (on Day 1) of twice the usual daily dose results in plasma concentrations close to steady-state by the second day. The apparent volume of distribution of fluconazole approximates that of total body water. Plasma protein binding is low (11 to 12%). Following either single- or multiple oral doses for up to 14 days, fluconazole penetrates into all body fluids studied (see table below). In normal volunteers, saliva concentrations of fluconazole were equal to or slightly greater than plasma concentrations regardless of dose, route, or duration of dosing. In patients with bronchiectasis, sputum concentrations of fluconazole following a single 150 mg oral dose were equal to plasma concentrations at both 4 and 24 hours post dose. In patients with fungal meningitis, fluconazole concentrations in the cerebrospinal fluid (CSF) are approximately 80% of the corresponding plasma concentrations.

A single oral 150 mg dose of fluconazole administered to 27 patients penetrated into vaginal tissue, resulting in tissue: plasma ratios ranging from 0.94 to 1.14 over the first 48 hours following dosing.

A single oral 150 mg dose of fluconazole administered to 14 patients penetrated into vaginal fluid, resulting in fluid: plasma ratios ranging from 0.36 to 0.71 over the first 72 hours following dosing.

Table 2: Ratio of Fluconazole Tissue (Fluid)/Plasma Concentration

Tissue or Fluid | Ratio of Fluconazole Tissue (Fluid)/Plasma Concentration [Relative to concurrent concentrations in plasma in subjects with normal renal function.]
Cerebrospinal fluid [Independent of degree of meningeal inflammation.] | 0.5–0.9
Saliva | 1
Sputum | 1
Blister fluid | 1
Urine | 10
Normal skin | 10
Nails | 1
Blister skin | 2
Vaginal tissue | 1
Vaginal fluid | 0.4–0.7

Mean body clearance in adults is reported to be 0.23 (17%) mL/min/kg. In normal volunteers, fluconazole is cleared primarily by renal excretion, with approximately 80% of the administered dose appearing in the urine as unchanged drug. About 11% of the dose is excreted in the urine as metabolites.

The pharmacokinetics of fluconazole are markedly affected by reduction in renal function. There is an inverse relationship between the elimination half-life and creatinine clearance. The dose of DIFLUCAN may need to be reduced in patients with impaired renal function. (See DOSAGE AND ADMINISTRATION.) A 3-hour hemodialysis session decreases plasma concentrations by approximately 50%.

In normal volunteers, DIFLUCAN administration (doses ranging from 200 mg to 400 mg once daily for up to 14 days) was associated with small and inconsistent effects on testosterone concentrations, endogenous corticosteroid concentrations, and the adrenocorticotropic hormone (ACTH)-stimulated cortisol response.

Pharmacokinetics in Pediatric Patients

In pediatric patients from 2 days to 15 years of age, the following pharmacokinetic data have been reported following the administration of DIFLUCAN:

Table 3: Pharmacokinetic Parameters* of Fluconazole in Pediatric Patients Following the Administration of DIFLUCAN

Age Studied | Dose (mg/kg) | Clearance (mL/min/kg) | Half-life (Hours) | Cmax (mcg/mL) | AUC (mcg*h/mL) | Vdss (L/kg)
2 to 60 days | IV 25 mg/kg on day one followed by; IV 12 mg/kg once daily | 0.29 (35%); N=8 | 54.2 | 23.4 (29%); N=8 | 439 (25%)^ | 1.13 (31%)
9 months to 13 years | Single-Oral 2 mg/kg | 0.40 (38%) N=14 | 25.0 | 2.9 (22%) N=16 | 94.7 (34%)*; N=14 | N/A
9 months to 13 years | Single-Oral 8 mg/kg | 0.51 (60%) N=15 | 19.5 | 9.8 (20%) N=15 | 362.5 (58%)*; N=14 | N/A
5 to 15 years | Multiple IV 2 mg/kg | 0.49 (40%) N=4 | 17.4 | 5.5 (25%) N=5 | 67.4 (26%)^; N=4 | 0.722 (36%) N=4
5 to 15 years | Multiple IV 4 mg/kg | 0.59 (64%) N=5 | 15.2 | 11.4 (44%) N=6 | 139.1 (46%)^; N=5 | 0.729 (33%) N=5
5 to 15 years | Multiple IV 8 mg/kg | 0.66 (31%) N=7 | 17.6 | 14.1 (22%) N=8 | 196.7 (25%)^; N=7 | 1.069 (37%) N=7

*Data for Clearance, Cmax, AUC and Vdss are presented as arithmetic mean (CV%) and Half-life as arithmetic mean only. *AUC0-inf; ^AUC0-24;

Abbreviations: Cmax=Peak plasma concentrations, AUC =area under the plasma concentration time curve; and Vdss=volume of distribution at steady state.

There are limited data available in patients 61 days to less than 9 months of age.

In pediatric patients (premature newborns; gestational age 26 to 29 weeks and postnatal age from birth to 1 day), the mean (%cv) clearance within 36 hours of birth was 0.180 (35%, N=7) mL/min/kg, which increased with time to a mean of 0.218 (31%, N=9) mL/min/kg 6 days later and 0.333 (56%, N=4) mL/min/kg 12 days later. Similarly, the half‑life was 73.6 hours, which decreased with time to a mean of 53.2 hours 6 days later and 46.6 hours 12 days later.

In a study of 13 pediatric patients (preterm and term infants with median gestational age of 37 weeks, GA range 24 to 39 weeks; median postnatal age [PNA] 19 days, PNA range: 5 to 262 days) 12 infants received a 25 mg/kg loading dose, and 9/12 (75%) achieved an AUC0-24 of >400-mg*h/L in the first 24 hours. A population pharmacokinetic model using data from 55 pediatric patients (GA 23 to 40 weeks, PNA 1- 88 days) found that a loading dose of 25 mg/kg is necessary to reach target AUC >400-mg*h/L within 24 hours of initiating therapy in pediatric patients younger than 3 months of age. A maintenance dose of 9 mg/kg daily should be used in pediatric patients born at GA less than 30 weeks and 12 mg/kg daily in pediatric patients with GA equal or greater than 30 weeks. (See DOSAGE AND ADMINISTRATION.)

A population PK model using data from 21 pediatric patients ages from birth to 17 years supported with extracorporeal membrane oxygenation (ECMO), and 19 pediatric non-ECMO patients ages from birth to 2 years found that clearance was related to serum creatinine while a higher volume of distribution was related to presence of ECMO support. The median volume of distribution was 1.3 L/kg in pediatric patients on ECMO and 0.9 L/kg in those not on ECMO. Simulations suggested that a loading dose of 35 mg/kg is needed to achieve the target AUC0-24 >400 mg*h/L within the first 24 hours in pediatric patients on ECMO. (See DOSAGE AND ADMINISTRATION.).

Pharmacokinetics in Elderly

A pharmacokinetic study was conducted in 22 subjects, 65 years of age or older receiving a single 50 mg oral dose of fluconazole. Ten of these patients were concomitantly receiving diuretics. The Cmax was 1.54 mcg/mL and occurred at 1.3 hours post dose. The mean AUC was 76.4 ± 20.3 mcg∙h/mL, and the mean terminal half-life was 46.2 hours. These pharmacokinetic parameter values are higher than analogous values reported for normal young male volunteers. Coadministration of diuretics did not significantly alter the AUC or Cmax. In addition, creatinine clearance (74 mL/min), the percent of drug recovered unchanged in urine (0 to 24 hours, 22%), and the fluconazole renal clearance estimates (0.124 mL/min/kg) for the elderly were generally lower than those of younger volunteers. Thus, the alteration of fluconazole disposition in the elderly appears to be related to reduced renal function characteristic of this group. A plot of each subject's terminal elimination half-life versus creatinine clearance compared to the predicted half-life – creatinine clearance curve derived from normal subjects and subjects with varying degrees of renal insufficiency indicated that 21 of 22 subjects fell within the 95% confidence limit of the predicted half-life-creatinine clearance curves. These results are consistent with the hypothesis that higher values for the pharmacokinetic parameters observed in the elderly subjects compared to normal young male volunteers are due to the decreased kidney function that is expected in the elderly.

Drug Interaction Studies

(See PRECAUTIONS, Drug Interactions)

Oral contraceptives:

Oral contraceptives were administered as a single dose both before and after the oral administration of DIFLUCAN 50 mg once daily for 10 days in 10 healthy women. There was no significant difference in ethinyl estradiol or levonorgestrel AUC after the administration of 50 mg of DIFLUCAN. The mean increase in ethinyl estradiol AUC was 6% (range: –47 to 108%) and levonorgestrel AUC increased 17% (range: –33 to 141%).

In a second study, twenty-five normal females received daily doses of both 200 mg DIFLUCAN tablets or placebo for two, ten-day periods. The treatment cycles were one month apart with all subjects receiving DIFLUCAN during one cycle and placebo during the other. The order of study treatment was random. Single doses of an oral contraceptive tablet containing levonorgestrel and ethinyl estradiol were administered on the final treatment day (Day 10) of both cycles. Following administration of 200 mg of DIFLUCAN, the mean percentage increase of AUC for levonorgestrel compared to placebo was 25% (range: –12 to 82%) and the mean percentage increase for ethinyl estradiol compared to placebo was 38% (range: –11 to 101%). Both of these increases were statistically significantly different from placebo.

A third study evaluated the potential interaction of once-weekly dosing of fluconazole 300 mg to 21 normal females taking an oral contraceptive containing ethinyl estradiol and norethindrone. In this placebo-controlled, double-blind, randomized, two-way crossover study carried out over three cycles of oral contraceptive treatment, fluconazole dosing resulted in small increases in the mean AUCs of ethinyl estradiol and norethindrone compared to similar placebo dosing. The mean AUCs of ethinyl estradiol and norethindrone increased by 24% (95% C.I. range: 18 to 31%) and 13% (95% C.I. range: 8 to 18%), respectively, relative to placebo. Fluconazole treatment did not cause a decrease in the ethinyl estradiol AUC of any individual subject in this study compared to placebo dosing. The individual AUC values of norethindrone decreased very slightly (<5%) in 3 of the 21 subjects after fluconazole treatment.

Cimetidine:

DIFLUCAN 100 mg was administered as a single oral dose alone and two hours after a single dose of cimetidine 400 mg to six healthy male volunteers. After the administration of cimetidine, there was a significant decrease in fluconazole AUC and Cmax. There was a mean ± SD decrease in fluconazole AUC of 13% ± 11% (range: –3.4 to –31%) and Cmax decreased 19% ± 14% (range: –5 to –40%). However, the administration of cimetidine 600 mg to 900 mg intravenously over a four-hour period (from one hour before to 3 hours after a single oral dose of DIFLUCAN 200 mg) did not affect the bioavailability or pharmacokinetics of fluconazole in 24 healthy male volunteers.

Antacid:

Administration of Maalox® (20 mL) to 14 normal male volunteers immediately prior to a single dose of DIFLUCAN 100 mg had no effect on the absorption or elimination of fluconazole.

Hydrochlorothiazide:

Concomitant oral administration of 100 mg DIFLUCAN and 50 mg hydrochlorothiazide for 10 days in 13 normal volunteers resulted in a significant increase in fluconazole AUC and Cmax compared to DIFLUCAN given alone. There was a mean ± SD increase in fluconazole AUC and Cmax of 45% ± 31% (range: 19 to 114%) and 43% ± 31% (range: 19 to 122%), respectively. These changes are attributed to a mean ± SD reduction in renal clearance of 30% ± 12% (range: –10 to –50%).

Rifampin:

Administration of a single oral 200 mg dose of DIFLUCAN after 15 days of rifampin administered as 600 mg daily in eight healthy male volunteers resulted in a significant decrease in fluconazole AUC and a significant increase in apparent oral clearance of fluconazole. There was a mean ± SD reduction in fluconazole AUC of 23% ± 9% (range: –13 to –42%). Apparent oral clearance of fluconazole increased 32% ± 17% (range: 16 to 72%). Fluconazole half-life decreased from 33.4 ± 4.4 hours to 26.8 ± 3.9 hours. (See PRECAUTIONS.)

Warfarin:

There was a significant increase in prothrombin time response (area under the prothrombin time-time curve) following a single dose of warfarin (15 mg) administered to 13 normal male volunteers following oral DIFLUCAN 200 mg administered daily for 14 days as compared to the administration of warfarin alone. There was a mean ± SD increase in the prothrombin time response (area under the prothrombin time-time curve) of 7% ± 4% (range: –2 to 13%). (See PRECAUTIONS.) Mean is based on data from 12 subjects as one of 13 subjects experienced a 2-fold increase in his prothrombin time response.

Phenytoin:

Phenytoin AUC was determined after 4 days of phenytoin dosing (200 mg daily, orally for 3 days followed by 250 mg intravenously for one dose) both with and without the administration of fluconazole (oral DIFLUCAN 200 mg daily for 16 days) in 10 normal male volunteers. There was a significant increase in phenytoin AUC. The mean ± SD increase in phenytoin AUC was 88% ± 68% (range: 16 to 247%). The absolute magnitude of this interaction is unknown because of the intrinsically nonlinear disposition of phenytoin. (See PRECAUTIONS.)

Cyclosporine:

Cyclosporine AUC and Cmax were determined before and after the administration of fluconazole 200 mg daily for 14 days in eight renal transplant patients who had been on cyclosporine therapy for at least 6 months and on a stable cyclosporine dose for at least 6 weeks. There was a significant increase in cyclosporine AUC, Cmax, Cmin (24-hour concentration), and a significant reduction in apparent oral clearance following the administration of fluconazole. The mean ± SD increase in AUC was 92% ± 43% (range: 18 to 147%). The Cmax increased 60% ± 48% (range: –5 to 133%). The Cmin increased 157% ± 96% (range: 33 to 360%). The apparent oral clearance decreased 45% ± 15% (range: –15 to –60%). (See PRECAUTIONS.)

Zidovudine:

Plasma zidovudine concentrations were determined on two occasions (before and following fluconazole 200 mg daily for 15 days) in 13 volunteers with AIDS or ARC who were on a stable zidovudine dose for at least two weeks. There was a significant increase in zidovudine AUC following the administration of fluconazole. The mean ± SD increase in AUC was 20% ± 32% (range: –27 to 104%). The metabolite, GZDV, to parent drug ratio significantly decreased after the administration of fluconazole, from 7.6 ± 3.6 to 5.7 ± 2.2.

Theophylline:

The pharmacokinetics of theophylline were determined from a single intravenous dose of aminophylline (6 mg/kg) before and after the oral administration of fluconazole 200 mg daily for 14 days in 16 normal male volunteers. There were significant increases in theophylline AUC, Cmax, and half-life with a corresponding decrease in clearance. The mean ± SD theophylline AUC increased 21% ± 16% (range: –5 to 48%). The Cmax increased 13% ± 17% (range: –13 to 40%). Theophylline clearance decreased 16% ± 11% (range: –32 to 5%). The half-life of theophylline increased from 6.6 ± 1.7 hours to 7.9 ± 1.5 hours. (See PRECAUTIONS.)

Quinidine:

Although not studied in vitro or in vivo, concomitant administration of fluconazole with quinidine may result in inhibition of quinidine metabolism. Use of quinidine has been associated with QT prolongation and rare occurrences of torsade de pointes. Coadministration of fluconazole and quinidine is contraindicated. (See CONTRAINDICATIONS and PRECAUTIONS.)

Oral hypoglycemics:

The effects of fluconazole on the pharmacokinetics of the sulfonylurea oral hypoglycemic agents tolbutamide, glipizide, and glyburide were evaluated in three placebo-controlled studies in normal volunteers. All subjects received the sulfonylurea alone as a single dose and again as a single dose following the administration of DIFLUCAN 100 mg daily for 7 days. In these three studies, 22/46 (47.8%) of DIFLUCAN-treated patients and 9/22 (40.1%) of placebo-treated patients experienced symptoms consistent with hypoglycemia. (See PRECAUTIONS.)

Tolbutamide:

In 13 normal male volunteers, there was significant increase in tolbutamide (500 mg single dose) AUC and Cmax following the administration of fluconazole. There was a mean ± SD increase in tolbutamide AUC of 26% ± 9% (range: 12 to 39%). Tolbutamide Cmax increased 11% ± 9% (range: –6 to 27%). (See PRECAUTIONS.)

Glipizide:

The AUC and Cmax of glipizide (2.5 mg single dose) were significantly increased following the administration of fluconazole in 13 normal male volunteers. There was a mean ± SD increase in AUC of 49% ± 13% (range: 27 to 73%) and an increase in Cmax of 19% ± 23% (range: –11 to 79%). (See PRECAUTIONS.)

Glyburide:

The AUC and Cmax of glyburide (5 mg single dose) were significantly increased following the administration of fluconazole in 20 normal male volunteers. There was a mean ± SD increase in AUC of 44% ± 29% (range: –13 to 115%) and Cmax increased 19% ± 19% (range: –23 to 62%). Five subjects required oral glucose following the ingestion of glyburide after 7 days of fluconazole administration. (See PRECAUTIONS.)

Rifabutin:

There have been published reports that an interaction exists when fluconazole is administered concomitantly with rifabutin, leading to increased serum levels of rifabutin. (See PRECAUTIONS.)

Tacrolimus:

There have been published reports that an interaction exists when fluconazole is administered concomitantly with tacrolimus, leading to increased serum levels of tacrolimus. (See PRECAUTIONS.)

Midazolam:

The effect of fluconazole on the pharmacokinetics and pharmacodynamics of midazolam was examined in a randomized, cross-over study in 12 volunteers. In the study, subjects ingested placebo or 400 mg fluconazole on Day 1 followed by 200 mg daily from Day 2 to Day 6. In addition, a 7.5 mg dose of midazolam was orally ingested on the first day, 0.05 mg/kg was administered intravenously on the fourth day, and 7.5 mg orally on the sixth day. Fluconazole reduced the clearance of IV midazolam by 51%. On the first day of dosing, fluconazole increased the midazolam AUC and Cmax by 259% and 150%, respectively. On the sixth day of dosing, fluconazole increased the midazolam AUC and Cmax by 259% and 74%, respectively. The psychomotor effects of midazolam were significantly increased after oral administration of midazolam but not significantly affected following intravenous midazolam.

A second randomized, double-dummy, placebo-controlled, cross over study in three phases was performed to determine the effect of route of administration of fluconazole on the interaction between fluconazole and midazolam. In each phase the subjects were given oral fluconazole 400 mg and intravenous saline; oral placebo and intravenous fluconazole 400 mg; and oral placebo and IV saline. An oral dose of 7.5 mg of midazolam was ingested after fluconazole/placebo. The AUC and Cmax of midazolam were significantly higher after oral than IV administration of fluconazole. Oral fluconazole increased the midazolam AUC and Cmax by 272% and 129%, respectively. IV fluconazole increased the midazolam AUC and Cmax by 244% and 79%, respectively. Both oral and IV fluconazole increased the pharmacodynamic effects of midazolam. (See PRECAUTIONS.)

Azithromycin:

An open-label, randomized, three-way crossover study in 18 healthy subjects assessed the effect of a single 800 mg oral dose of fluconazole on the pharmacokinetics of a single 1200 mg oral dose of azithromycin as well as the effects of azithromycin on the pharmacokinetics of fluconazole. There was no significant pharmacokinetic interaction between fluconazole and azithromycin.

Voriconazole:

Voriconazole is a substrate for both CYP2C9 and CYP3A4 isoenzymes. Concurrent administration of oral Voriconazole (400 mg Q12h for 1 day, then 200 mg Q12h for 2.5 days) and oral fluconazole (400 mg on Day 1, then 200 mg Q24h for 4 days) to 6 healthy male subjects resulted in an increase in Cmax and AUCτ of voriconazole by an average of 57% (90% CI: 20% to 107%) and 79% (90% CI: 40% to 128%), respectively. In a follow-on clinical study involving 8 healthy male subjects, reduced dosing and/or frequency of voriconazole and fluconazole did not eliminate or diminish this effect. (See PRECAUTIONS.)

Tofacitinib:

Coadministration of fluconazole (400 mg on Day 1 and 200 mg once daily for 6 days [Days 2–7]) and tofacitinib (30 mg single dose on Day 5) in healthy subjects resulted in increased mean tofacitinib AUC and Cmax values of approximately 79% (90% CI: 64% to 96%) and 27% (90% CI: 12% to 44%), respectively, compared to administration of tofacitinib alone. (See PRECAUTIONS.)

Abrocitinib:

When coadministered with fluconazole (inhibitor of CYP2C9, 2C19, and 3A4), the systemic exposure (AUC) of abrocitinib was approximately 4.8-fold higher and the combined exposure (AUC) of abrocitinib and its active metabolites was approximately 2.5-fold higher compared to when abrocitinib was administered alone. (See PRECAUTIONS).

Microbiology

Mechanism of Action

Fluconazole is a highly selective inhibitor of fungal cytochrome P450 dependent enzyme lanosterol 14-α-demethylase. This enzyme functions to convert lanosterol to ergosterol. The subsequent loss of normal sterols correlates with the accumulation of 14-α-methyl sterols in fungi and may be responsible for the fungistatic activity of fluconazole. Mammalian cell demethylation is much less sensitive to fluconazole inhibition.

Resistance

A potential for development of resistance to fluconazole is well known. Fungal isolates exhibiting reduced susceptibility to other azoles may also show reduced susceptibility to fluconazole. The frequency of drug resistance development for the various fungi for which this drug is indicated is not known.

Fluconazole resistance may arise from a modification in the quality or quantity of the target enzyme (lanosterol 14-α-demethylase), reduced access to the drug target, or some combination of these mechanisms.

Point mutations in the gene (ERG11) encoding for the target enzyme lead to an altered target with decreased affinity for azoles. Overexpression of ERG11 results in the production of high concentrations of the target enzyme, creating the need for higher intracellular drug concentrations to inhibit all of the enzyme molecules in the cell.

The second major mechanism of drug resistance involves active efflux of fluconazole out of the cell through the activation of two types of multidrug efflux transporters; the major facilitators (encoded by MDR genes) and those of the ATP-binding cassette superfamily (encoded by CDR genes). Upregulation of the MDR gene leads to fluconazole resistance, whereas, upregulation of CDR genes may lead to resistance to multiple azoles.

Resistance in Candida glabrata usually includes upregulation of CDR genes resulting in resistance to multiple azoles. For an isolate where the minimum inhibitory concentration (MIC) is categorized as Intermediate (16 to 32 mcg/mL), the highest fluconazole dose is recommended.

Antimicrobial Activity

Fluconazole has been shown to be active against most isolates of the following microorganisms both in vitro and in clinical infections.

Candida albicans
Candida glabrata (Many isolates are intermediately susceptible)
Candida parapsilosis
Candida tropicalis
Cryptococcus neoformans

The following in vitro data are available, but their clinical significance is unknown. At least 90% of the following fungi exhibit an in vitro MIC less than or equal to the susceptible breakpoint for fluconazole (https://www.fda.gov/STIC) against isolates of similar genus or organism group. However, the effectiveness of fluconazole in treating clinical infections due to these fungi has not been established in adequate and well-controlled clinical trials.

Candida dubliniensis
Candida guilliermondii
Candida kefyr
Candida lusitaniae

Candida krusei should be considered to be resistant to fluconazole. Resistance in C. krusei appears to be mediated by reduced sensitivity of the target enzyme to inhibition by the agent.

Susceptibility Testing

For specific information regarding susceptibility test interpretive criteria and associated test methods and quality control standards recognized by FDA for this drug, please see: https://www.fda.gov/STIC.

INDICATIONS AND USAGE

DIFLUCAN (fluconazole) is indicated for the treatment of:

1. Vaginal candidiasis (vaginal yeast infections due to Candida).
2. Oropharyngeal and esophageal candidiasis. In open noncomparative studies of relatively small numbers of patients, DIFLUCAN was also effective for the treatment of Candida urinary tract infections, peritonitis, and systemic Candida infections including candidemia, disseminated candidiasis, and pneumonia.
3. Cryptococcal meningitis. Before prescribing DIFLUCAN (fluconazole) for AIDS patients with cryptococcal meningitis, please see CLINICAL STUDIES section. Studies comparing DIFLUCAN to amphotericin B in non-HIV infected patients have not been conducted.

Prophylaxis:

DIFLUCAN is also indicated to decrease the incidence of candidiasis in patients undergoing bone marrow transplantation who receive cytotoxic chemotherapy and/or radiation therapy.

Specimens for fungal culture and other relevant laboratory studies (serology, histopathology) should be obtained prior to therapy to isolate and identify causative organisms. Therapy may be instituted before the results of the cultures and other laboratory studies are known; however, once these results become available, anti-infective therapy should be adjusted accordingly.

CLINICAL STUDIES

Cryptococcal meningitis:

In a multicenter study comparing DIFLUCAN (200 mg/day) to amphotericin B (0.3 mg/kg/day) for treatment of cryptococcal meningitis in patients with AIDS, a multivariate analysis revealed three pretreatment factors that predicted death during the course of therapy: abnormal mental status, cerebrospinal fluid cryptococcal antigen titer greater than 1:1024, and cerebrospinal fluid white blood cell count of less than 20 cells/mm^3. Mortality among high risk patients was 33% and 40% for amphotericin B and DIFLUCAN patients, respectively (p=0.58), with overall deaths 14% (9 of 63 subjects) and 18% (24 of 131 subjects) for the 2 arms of the study (p=0.48). Optimal doses and regimens for patients with acute cryptococcal meningitis and at high risk for treatment failure remain to be determined. (Saag, et al. N Engl J Med 1992; 326:83-9.)

Vaginal candidiasis:

Two adequate and well-controlled studies were conducted in the U.S. using the 150 mg tablet. In both, the results of the fluconazole regimen were comparable to the control regimen (clotrimazole or miconazole intravaginally for 7 days) both clinically and statistically at the one month post-treatment evaluation.

The therapeutic cure rate, defined as a complete resolution of signs and symptoms of vaginal candidiasis (clinical cure), along with a negative KOH examination and negative culture for Candida (microbiologic eradication), was 55% in both the fluconazole group and the vaginal products group.

 | Fluconazole PO 150 mg tablet | Vaginal Product qhs × 7 days
Enrolled | 448 | 422
Evaluable at Late Follow-up | 347 (77%) | 327 (77%)
Clinical cure | 239/347 (69%) | 235/327 (72%)
Mycologic eradication | 213/347 (61%) | 196/327 (60%)
Therapeutic cure | 190/347 (55%) | 179/327 (55%)

Approximately three-fourths of the enrolled patients had acute vaginitis (<4 episodes/12 months) and achieved 80% clinical cure, 67% mycologic eradication, and 59% therapeutic cure when treated with a 150 mg DIFLUCAN tablet administered orally. These rates were comparable to control products. The remaining one-fourth of enrolled patients had recurrent vaginitis (≥4 episodes/12 months) and achieved 57% clinical cure, 47% mycologic eradication, and 40% therapeutic cure. The numbers are too small to make meaningful clinical or statistical comparisons with vaginal products in the treatment of patients with recurrent vaginitis.

Substantially more gastrointestinal events were reported in the fluconazole group compared to the vaginal product group. Most of the events were mild to moderate. Because fluconazole was given as a single dose, no discontinuations occurred.

Parameter | Fluconazole PO | Vaginal Products
Evaluable patients | 448 | 422
With any adverse event | 141 (31%) | 112 (27%)
Nervous System | 90 (20%) | 69 (16%)
Gastrointestinal | 73 (16%) | 18 (4%)
With drug-related event | 117 (26%) | 67 (16%)
Nervous System | 61 (14%) | 29 (7%)
Headache | 58 (13%) | 28 (7%)
Gastrointestinal | 68 (15%) | 13 (3%)
Abdominal pain | 25 (6%) | 7 (2%)
Nausea | 30 (7%) | 3 (1%)
Diarrhea | 12 (3%) | 2 (<1%)
Application site event | 0 (0%) | 19 (5%)
Taste Perversion | 6 (1%) | 0 (0%)

Pediatric Studies

Oropharyngeal candidiasis:

An open-label, comparative study of the efficacy and safety of DIFLUCAN (2 to 3 mg/kg/day) and oral nystatin (400,000 I.U. 4 times daily) was conducted in immunocompromised pediatric patients from 6 months to 13 years of age with oropharyngeal candidiasis. Clinical and mycological response rates were higher in pediatric patients treated with fluconazole.

Clinical cure at the end of treatment was reported for 86% of fluconazole-treated patients compared to 46% of nystatin treated patients. Mycologically, 76% of fluconazole treated patients had the infecting organism eradicated compared to 11% for nystatin treated patients.

 | Fluconazole | Nystatin
Enrolled | 96 | 90
Clinical Cure | 76/88 (86%) | 36/78 (46%)
Mycological eradication [Subjects without follow-up cultures for any reason were considered nonevaluable for mycological response.] | 55/72 (76%) | 6/54 (11%)

The proportion of patients with clinical relapse 2 weeks after the end of treatment was 14% for subjects receiving DIFLUCAN and 16% for subjects receiving nystatin. At 4 weeks after the end of treatment, the percentages of patients with clinical relapse were 22% for DIFLUCAN and 23% for nystatin.

CONTRAINDICATIONS

DIFLUCAN (fluconazole) is contraindicated in patients who have shown hypersensitivity to fluconazole or to any of its excipients. There is no information regarding cross-hypersensitivity between fluconazole and other azole antifungal agents. Caution should be used in prescribing DIFLUCAN to patients with hypersensitivity to other azoles. Coadministration of other drugs known to prolong the QT interval and which are metabolized via the enzyme CYP3A4 such as erythromycin, pimozide, and quinidine are contraindicated in patients receiving fluconazole. (See CLINICAL PHARMACOLOGY: Drug Interaction Studies and PRECAUTIONS.)

WARNINGS

(1) Hepatic injury: DIFLUCAN should be administered with caution to patients with liver dysfunction. DIFLUCAN has been associated with rare cases of serious hepatic toxicity, including fatalities primarily in patients with serious underlying medical conditions. In cases of DIFLUCAN-associated hepatotoxicity, no obvious relationship to total daily dose, duration of therapy, sex, or age of the patient has been observed. DIFLUCAN hepatotoxicity has usually, but not always, been reversible on discontinuation of therapy. Patients who develop abnormal liver function tests during DIFLUCAN therapy should be monitored for the development of more severe hepatic injury. DIFLUCAN should be discontinued if clinical signs and symptoms consistent with liver disease develop that may be attributable to DIFLUCAN.

(2) Anaphylaxis: In rare cases, anaphylaxis has been reported.

(3) Dermatologic: Exfoliative skin disorders during treatment with DIFLUCAN have been reported. Fatal outcomes have been reported in patients with serious underlying diseases. Patients with deep seated fungal infections who develop rashes during treatment with DIFLUCAN should be monitored closely and the drug discontinued if lesions progress. Fluconazole should be discontinued in patients treated for superficial fungal infection who develop a rash that may be attributed to fluconazole.

(4) Potential for fetal harm: There are no adequate and well-controlled clinical trials of DIFLUCAN in pregnant women. Case reports describe a pattern of distinct congenital anomalies in infants exposed in utero to high dose maternal fluconazole (400 to 800 mg/day) during most or all of the first trimester. These reported anomalies are similar to those seen in animal studies. If DIFLUCAN is used during pregnancy or if the patient becomes pregnant while taking the drug, the patient should be informed of the potential hazard to the fetus. Effective contraceptive measures should be considered in women of child-bearing potential who are being treated with DIFLUCAN 400 to 800 mg/day and should continue throughout the treatment period and for approximately 1 week (5 to 6 half-lives) after the final dose. Epidemiological studies suggest a potential risk of spontaneous abortion and congenital abnormalities in infants whose mothers were treated with 150 mg of fluconazole as a single or repeated dose in the first trimester, but these epidemiological studies have limitations and these findings have not been confirmed in controlled clinical trials. (See PRECAUTIONS: Pregnancy.)

PRECAUTIONS

General

Some azoles, including fluconazole, have been associated with prolongation of the QT interval on the electrocardiogram. Fluconazole causes QT prolongation via the inhibition of Rectifier Potassium Channel current (Ikr). The QT prolongation caused by other medicinal products (such as amiodarone) may be amplified via the inhibition of cytochrome P450 (CYP) 3A4. (See PRECAUTIONS: Drug Interactions.) During post-marketing surveillance, there have been rare cases of QT prolongation and torsade de pointes in patients taking fluconazole. Most of these reports involved seriously ill patients with multiple confounding risk factors, such as structural heart disease, electrolyte abnormalities, and concomitant medications that may have been contributory. Patients with hypokalemia and advanced cardiac failure are at an increased risk for the occurrence of life-threatening ventricular arrhythmias and torsade de pointes.

Fluconazole should be administered with caution to patients with these potentially proarrhythmic conditions.

Concomitant use of fluconazole and erythromycin has the potential to increase the risk of cardiotoxicity (prolonged QT interval, torsade de pointes) and consequently sudden heart death. This combination should be avoided.

Fluconazole should be administered with caution to patients with renal dysfunction.

Adrenal insufficiency has been reported in patients receiving azoles, including fluconazole. Reversible cases of adrenal insufficiency have been reported in patients receiving fluconazole.

DIFLUCAN Powder for Oral Suspension contains sucrose and should not be used in patients with hereditary fructose, glucose/galactose malabsorption, and sucrase-isomaltase deficiency.

When driving vehicles or operating machines, it should be taken into account that occasionally dizziness or seizures may occur.

There have been reports of cases of superinfection with Candida species other than C. albicans, which are often inherently not susceptible to DIFLUCAN (e.g., Candida krusei). Such cases may require alternative antifungal therapy (see CLINICAL PHARMACOLOGY, Microbiology).

Single Dose

The convenience and efficacy of the single dose oral tablet of fluconazole regimen for the treatment of vaginal yeast infections should be weighed against the acceptability of a higher incidence of drug related adverse events with DIFLUCAN (26%) versus intravaginal agents (16%) in U.S. comparative clinical studies. (See ADVERSE REACTIONS and CLINICAL STUDIES.)

Drug Interactions:

(See CONTRAINDICATIONS.) Fluconazole is a moderate CYP2C9 and CYP3A4 inhibitor. Fluconazole is also a strong inhibitor of CYP2C19. Patients treated with DIFLUCAN, who are also concomitantly treated with drugs with a narrow therapeutic window metabolized through CYP2C9 and CYP3A4, should be monitored for adverse reactions associated with the concomitantly administered drugs. In addition to the observed /documented interactions mentioned below, there is a risk of increased plasma concentration of other compounds metabolized by CYP2C9, CYP2C19, and CYP3A4 coadministered with fluconazole. Therefore, caution should be exercised when using these combinations and the patients should be carefully monitored. The enzyme inhibiting effect of fluconazole persists 4 to 5 days after discontinuation of fluconazole treatment due to the long half-life of fluconazole. Clinically or potentially significant drug interactions between DIFLUCAN and the following agents/classes have been observed and are described in greater detail below:

Abrocitinib:

Drug interaction studies indicate that when coadministered with fluconazole (strong inhibitor of CYP2C19; moderate inhibitor of CYP2C9 and CYP3A4), the systemic exposure of abrocitinib and its active metabolites increased (See CLINICAL PHARMACOLOGY). Avoid concomitant use of abrocitinib with DIFLUCAN. Refer to the abrocitinib Prescribing Information for additional details.

Alfentanil:

A study observed a reduction in clearance and distribution volume as well as prolongation of t½ of alfentanil following concomitant treatment with fluconazole. A possible mechanism of action is fluconazole's inhibition of CYP3A4. Dosage adjustment of alfentanil may be necessary.

Amiodarone:

Concomitant administration of fluconazole with amiodarone may increase QT prolongation. Caution must be exercised if the concomitant use of fluconazole and amiodarone is necessary, notably with high-dose fluconazole (800 mg).

Amitriptyline, nortriptyline:

Fluconazole increases the effect of amitriptyline and nortriptyline. 5-Nortriptyline and/or S-amitriptyline may be measured at initiation of the combination therapy and after 1 week. Dosage of amitriptyline/nortriptyline should be adjusted, if necessary.

Amphotericin B:

Concurrent administration of fluconazole and amphotericin B in infected normal and immunosuppressed mice showed the following results: a small additive antifungal effect in systemic infection with Candida albicans, no interaction in intracranial infection with Cryptococcus neoformans, and antagonism of the two drugs in systemic infection with A. fumigatus. The clinical significance of results obtained in these studies is unknown.

Azithromycin:

An open-label, randomized, three-way crossover study in 18 healthy subjects assessed the effect of a single 1200 mg oral dose of azithromycin on the pharmacokinetics of a single 800 mg oral dose of fluconazole as well as the effects of fluconazole on the pharmacokinetics of azithromycin. There was no significant pharmacokinetic interaction between fluconazole and azithromycin.

Calcium channel blockers:

Certain calcium channel antagonists (nifedipine, isradipine, amlodipine, verapamil, and felodipine) are metabolized by CYP3A4. Fluconazole has the potential to increase the systemic exposure of the calcium channel antagonists. Frequent monitoring for adverse events is recommended.

Carbamazepine:

Fluconazole inhibits the metabolism of carbamazepine and an increase in serum carbamazepine of 30% has been observed. There is a risk of developing carbamazepine toxicity. Dosage adjustment of carbamazepine may be necessary depending on concentration measurements/effect.

Celecoxib:

During concomitant treatment with fluconazole (200 mg daily) and celecoxib (200 mg), the celecoxib Cmax and AUC increased by 68% and 134%, respectively. Half of the celecoxib dose may be necessary when combined with fluconazole.

Coumarin-type anticoagulants:

Prothrombin time may be increased in patients receiving concomitant DIFLUCAN and coumarin-type anticoagulants. In post-marketing experience, as with other azole antifungals, bleeding events (bruising, epistaxis, gastrointestinal bleeding, hematuria, and melena) have been reported in association with increases in prothrombin time in patients receiving fluconazole concurrently with warfarin. Careful monitoring of prothrombin time in patients receiving DIFLUCAN and coumarin-type anticoagulants is recommended. Dose adjustment of warfarin may be necessary. (See CLINICAL PHARMACOLOGY: Drug Interaction Studies.)

Cyclophosphamide:

Combination therapy with cyclophosphamide and fluconazole results in an increase in serum bilirubin and serum creatinine. The combination may be used while taking increased consideration to the risk of increased serum bilirubin and serum creatinine.

Cyclosporine:

DIFLUCAN significantly increases cyclosporine levels in renal transplant patients with or without renal impairment. Careful monitoring of cyclosporine concentrations and serum creatinine is recommended in patients receiving DIFLUCAN and cyclosporine. (See CLINICAL PHARMACOLOGY: Drug Interaction Studies.) This combination may be used by reducing the dosage of cyclosporine depending on cyclosporine concentration.

Fentanyl:

One fatal case of possible fentanyl-fluconazole interaction was reported. The author judged that the patient died from fentanyl intoxication. Furthermore, in a randomized crossover study with 12 healthy volunteers, it was shown that fluconazole delayed the elimination of fentanyl significantly. Elevated fentanyl concentration may lead to respiratory depression.

HMG-CoA reductase inhibitors:

The risk of myopathy and rhabdomyolysis increases when fluconazole is coadministered with HMG-CoA reductase inhibitors metabolized through CYP3A4, such as atorvastatin and simvastatin, or through CYP2C9, such as fluvastatin (decreased hepatic metabolism of the statin). If concomitant therapy is necessary, the patient should be observed for symptoms of myopathy and rhabdomyolysis and creatinine kinase should be monitored. HMG-CoA reductase inhibitors should be discontinued if a marked increase in creatinine kinase is observed or myopathy/rhabdomyolysis is diagnosed or suspected. Dose reduction of statins may be needed. Refer to the statin-specific prescribing information for details.

Hydrochlorothiazide:

In a pharmacokinetic interaction study, coadministration of multiple-dose hydrochlorothiazide to healthy volunteers receiving fluconazole increased plasma concentrations of fluconazole by 40%. An effect of this magnitude should not necessitate a change in the fluconazole dose regimen in subjects receiving concomitant diuretics.

Ibrutinib:

Moderate inhibitors of CYP3A4 such as fluconazole may increase plasma ibrutinib concentrations and increase risk of adverse reactions associated with ibrutinib. If ibrutinib and fluconazole are concomitantly administered, reduce the dose of ibrutinib as instructed in ibrutinib prescribing information and the patient should be frequently monitored for any adverse reactions associated with ibrutinib.

Ivacaftor and fixed dose ivacaftor combinations (e.g., tezacaftor/ivacaftor and ivacaftor/tezacaftor/elexacaftor):

Coadministration with ivacaftor, a cystic fibrosis transmembrane conductance regulator (CFTR) potentiator, increased ivacaftor exposure by 3-fold. If used concomitantly with a moderate inhibitor of CYP3A4, such as fluconazole, a reduction in the dose of ivacaftor (or ivacaftor combination) is recommended as instructed in the ivacaftor (or ivacaftor combination) prescribing information.

Lemborexant:

Concomitant administration of fluconazole increased lemborexant Cmax and AUC by approximately 1.6- and 4.2-fold, respectively which is expected to increase risk of adverse reactions, such as somnolence. Avoid concomitant use of DIFLUCAN with lemborexant.

Losartan:

Fluconazole inhibits the metabolism of losartan to its active metabolite (E-31 74) which is responsible for most of the angiotensin Il-receptor antagonism which occurs during treatment with losartan. Patients should have their blood pressure monitored continuously.

Lurasidone:

Concomitant use of moderate inhibitors of CYP3A4 such as fluconazole may increase lurasidone plasma concentrations. If concomitant use cannot be avoided, reduce the dose of lurasidone as instructed in the lurasidone prescribing information.

Methadone:

Fluconazole may enhance the serum concentration of methadone. Dosage adjustment of methadone may be necessary.

Non-steroidal anti-inflammatory drugs:

The Cmax and AUC of flurbiprofen were increased by 23% and 81%, respectively, when coadministered with fluconazole compared to administration of flurbiprofen alone. Similarly, the Cmax and AUC of the pharmacologically active isomer [S-(+)-ibuprofen] were increased by 15% and 82%, respectively, when fluconazole was coadministered with racemic ibuprofen (400 mg) compared to administration of racemic ibuprofen alone.

Although not specifically studied, fluconazole has the potential to increase the systemic exposure of other non-steroidal anti-inflammatory drugs (NSAIDs) that are metabolized by CYP2C9 (e.g., naproxen, lornoxicam, meloxicam, diclofenac). Frequent monitoring for adverse events and toxicity related to NSAIDs is recommended. Adjustment of dosage of NSAIDs may be needed.

Olaparib:

Moderate inhibitors of CYP3A4 such as fluconazole increase olaparib plasma concentrations; concomitant use is not recommended. If the combination cannot be avoided, reduce the dose of olaparib as instructed in the LYNPARZA® (Olaparib) Prescribing Information.

Oral contraceptives:

Two pharmacokinetic studies with a combined oral contraceptive have been performed using multiple doses of fluconazole. There were no relevant effects on hormone level in the 50 mg fluconazole study, while at 200 mg daily, the AUCs of ethinyl estradiol and levonorgestrel were increased 40% and 24%, respectively. Thus, multiple-dose use of fluconazole at these doses is unlikely to have an effect on the efficacy of the combined oral contraceptive.

Oral hypoglycemics:

Clinically significant hypoglycemia may be precipitated by the use of DIFLUCAN with oral hypoglycemic agents; one fatality has been reported from hypoglycemia in association with combined DIFLUCAN and glyburide use. DIFLUCAN reduces the metabolism of tolbutamide, glyburide, and glipizide and increases the plasma concentration of these agents. When DIFLUCAN is used concomitantly with these or other sulfonylurea oral hypoglycemic agents, blood glucose concentrations should be carefully monitored and the dose of the sulfonylurea should be adjusted as necessary. (See CLINICAL PHARMACOLOGY: Drug Interaction Studies.)

Phenytoin:

DIFLUCAN increases the plasma concentrations of phenytoin. Careful monitoring of phenytoin concentrations in patients receiving DIFLUCAN and phenytoin is recommended. (See CLINICAL PHARMACOLOGY: Drug Interaction Studies.)

Pimozide:

Although not studied in vitro or in vivo, concomitant administration of fluconazole with pimozide may result in inhibition of pimozide metabolism. Increased pimozide plasma concentrations can lead to QT prolongation and rare occurrences of torsade de pointes. Coadministration of fluconazole and pimozide is contraindicated.

Prednisone:

There was a case report that a liver-transplanted patient treated with prednisone developed acute adrenal cortex insufficiency when a 3 month therapy with fluconazole was discontinued. The discontinuation of fluconazole presumably caused an enhanced CYP3A4 activity which led to increased metabolism of prednisone. Patients on long-term treatment with fluconazole and prednisone should be carefully monitored for adrenal cortex insufficiency when fluconazole is discontinued.

Quinidine:

Although not studied in vitro or in vivo, concomitant administration of fluconazole with quinidine may result in inhibition of quinidine metabolism. Use of quinidine has been associated with QT prolongation and rare occurrences of torsade de pointes. Coadministration of fluconazole and quinidine is contraindicated. (See CONTRAINDICATIONS.)

Rifabutin:

There have been reports that an interaction exists when fluconazole is administered concomitantly with rifabutin, leading to increased serum levels of rifabutin up to 80%. There have been reports of uveitis in patients to whom fluconazole and rifabutin were coadministered. Patients receiving rifabutin and fluconazole concomitantly should be carefully monitored. (See CLINICAL PHARMACOLOGY: Drug Interaction Studies.)

Rifampin:

Rifampin enhances the metabolism of concurrently administered DIFLUCAN. Depending on clinical circumstances, consideration should be given to increasing the dose of DIFLUCAN when it is administered with rifampin. (See CLINICAL PHARMACOLOGY: Drug Interaction Studies.)

Saquinavir:

Fluconazole increases the AUC of saquinavir by approximately 50%, Cmax by approximately 55%, and decreases the clearance of saquinavir by approximately 50% due to inhibition of saquinavir's hepatic metabolism by CYP3A4 and inhibition of P-glycoprotein. Dosage adjustment of saquinavir may be necessary.

Short-acting benzodiazepines:

Following oral administration of midazolam, fluconazole resulted in substantial increases in midazolam concentrations and psychomotor effects. This effect on midazolam appears to be more pronounced following oral administration of fluconazole than with fluconazole administered intravenously. If short-acting benzodiazepines, which are metabolized by the cytochrome P450 system, are concomitantly administered with fluconazole, consideration should be given to decreasing the benzodiazepine dosage, and the patients should be appropriately monitored. (See CLINICAL PHARMACOLOGY: Drug Interaction Studies.)

Sirolimus:

Fluconazole increases plasma concentrations of sirolimus presumably by inhibiting the metabolism of sirolimus via CYP3A4 and P-glycoprotein. This combination may be used with a dosage adjustment of sirolimus depending on the effect/concentration measurements.

Tacrolimus:

Fluconazole may increase the serum concentrations of orally administered tacrolimus up to 5 times due to inhibition of tacrolimus metabolism through CYP3A4 in the intestines. No significant pharmacokinetic changes have been observed when tacrolimus is given intravenously. Increased tacrolimus levels have been associated with nephrotoxicity. Dosage of orally administered tacrolimus should be decreased depending on tacrolimus concentration. (See CLINICAL PHARMACOLOGY: Drug Interaction Studies.)

Theophylline:

DIFLUCAN increases the serum concentrations of theophylline. Careful monitoring of serum theophylline concentrations in patients receiving DIFLUCAN and theophylline is recommended. (See CLINICAL PHARMACOLOGY: Drug Interaction Studies.)

Tofacitinib:

Systemic exposure to tofacitinib is increased when tofacitinib is coadministered with fluconazole. Reduce the dose of tofacitinib when given concomitantly with fluconazole (i.e., from 5 mg twice daily to 5 mg once daily as instructed in the XELJANZ® [tofacitinib] label). (See CLINICAL PHARMACOLOGY: Drug Interaction Studies.)

Tolvaptan:

Plasma exposure to tolvaptan is significantly increased (200% in AUC; 80% in Cmax) when tolvaptan, a CYP3A4 substrate, is coadministered with fluconazole, a moderate CYP3A4 inhibitor. This interaction may result in the risk of a significant increase in adverse reactions associated with tolvaptan, particularly significant diuresis, dehydration, and acute renal failure. If tolvaptan and fluconazole are concomitantly administered, the tolvaptan dose should be reduced as instructed in the tolvaptan prescribing information and the patient should be frequently monitored for any adverse reactions associated with tolvaptan.

Triazolam:

Fluconazole increases the AUC of triazolam (single dose) by approximately 50%, Cmax by 20% to 32%, and increases t½ by 25% to 50 % due to the inhibition of metabolism of triazolam. Dosage adjustments of triazolam may be necessary.

Vinca alkaloids:

Although not studied, fluconazole may increase the plasma levels of the vinca alkaloids (e.g., vincristine and vinblastine) and lead to neurotoxicity, which is possibly due to an inhibitory effect on CYP3A4.

Vitamin A:

Based on a case report in one patient receiving combination therapy with all-trans-retinoid acid (an acid form of vitamin A) and fluconazole, central nervous system (CNS) related undesirable effects have developed in the form of pseudotumor cerebri, which disappeared after discontinuation of fluconazole treatment. This combination may be used but the incidence of CNS related undesirable effects should be borne in mind.

Voriconazole:

Avoid concomitant administration of voriconazole and fluconazole. Monitoring for adverse events and toxicity related to voriconazole is recommended; especially, if voriconazole is started within 24 h after the last dose of fluconazole. (See CLINICAL PHARMACOLOGY: Drug Interaction Studies.)

Zidovudine:

Fluconazole increases the Cmax and AUC of zidovudine by 84% and 74%, respectively, due to an approximately 45% decrease in oral zidovudine clearance. The half-life of zidovudine was likewise prolonged by approximately 128% following combination therapy with fluconazole. Patients receiving this combination should be monitored for the development of zidovudine-related adverse reactions. Dosage reduction of zidovudine may be considered.

Physicians should be aware that interaction studies with medications other than those listed in the CLINICAL PHARMACOLOGY section have not been conducted, but such interactions may occur.

Carcinogenesis, Mutagenesis, and Impairment of Fertility

Fluconazole showed no evidence of carcinogenic potential in mice and rats treated orally for 24 months at doses of 2.5 mg/kg/day, 5 mg/kg/day, or 10 mg/kg/day (approximately 2 to 7 times the recommended human dose). Male rats treated with 5 mg/kg/day and 10 mg/kg/day had an increased incidence of hepatocellular adenomas.

Fluconazole, with or without metabolic activation, was negative in tests for mutagenicity in four strains of S. typhimurium, and in the mouse lymphoma L5178Y system. Cytogenetic studies in vivo (murine bone marrow cells, following oral administration of fluconazole) and in vitro (human lymphocytes exposed to fluconazole at 1000 mcg/mL) showed no evidence of chromosomal mutations.

Fluconazole did not affect the fertility of male or female rats treated orally with daily doses of 5 mg/kg, 10 mg/kg, or 20 mg/kg or with parenteral doses of 5 mg/kg, 25 mg/kg, or 75 mg/kg, although the onset of parturition was slightly delayed at 20 mg/kg PO. In an intravenous perinatal study in rats at 5 mg/kg, 20 mg/kg, and 40 mg/kg, dystocia and prolongation of parturition were observed in a few dams at 20 mg/kg (approximately 5 to 15 times the recommended human dose) and 40 mg/kg, but not at 5 mg/kg. The disturbances in parturition were reflected by a slight increase in the number of still born pups and decrease of neonatal survival at these dose levels. The effects on parturition in rats are consistent with the species specific estrogen-lowering property produced by high doses of fluconazole. Such a hormone change has not been observed in women treated with fluconazole. (See CLINICAL PHARMACOLOGY.)

Pregnancy

Teratogenic Effects

Potential for Fetal Harm:

Use in pregnancy should be avoided except in patients with severe or potentially life-threatening fungal infections in whom fluconazole may be used if the anticipated benefit outweighs the possible risk to the fetus. A few published case reports describe a pattern of distinct congenital anomalies in infants exposed in utero to high dose maternal fluconazole (400 to 800 mg/day) during most or all of the first trimester. These reported anomalies are similar to those seen in animal studies. Effective contraceptive measures should be considered in women of child-bearing potential who are being treated with DIFLUCAN 400 to 800 mg/day and should continue throughout the treatment period and for approximately 1 week (5 to 6 half-lives) after the final dose. If DIFLUCAN is used during pregnancy, or if the patient becomes pregnant while taking the drug, the patient should be informed of the potential hazard to the fetus. Spontaneous abortions and congenital abnormalities have been suggested as potential risks associated with 150 mg of fluconazole as a single or repeated dose in the first trimester of pregnancy based on retrospective epidemiological studies. There are no adequate and well-controlled studies of DIFLUCAN in pregnant women. (See WARNINGS: Potential for Fetal Harm.)

Human Data

Case reports describe a distinctive and rare pattern of birth defects among infants whose mothers received high-dose (400 to 800 mg/day) fluconazole during most or all of the first trimester of pregnancy. The features seen in these infants include brachycephaly, abnormal facies, abnormal calvarial development, cleft palate, femoral bowing, thin ribs and long bones, arthrogryposis, and congenital heart disease. These effects are similar to those seen in animal studies.

Epidemiological studies suggest a potential risk of spontaneous abortion and congenital abnormalities in infants whose mothers were treated with 150 mg of fluconazole as a single or repeated dose in the first trimester, but these epidemiological studies have limitations and these findings have not been confirmed in controlled clinical trials.

Animal Data

Fluconazole was administered orally to pregnant rabbits during organogenesis in two studies at doses of 5 mg/kg, 10 mg/kg, and 20 mg/kg and at 5 mg/kg, 25 mg/kg, and 75 mg/kg, respectively. Maternal weight gain was impaired at all dose levels (approximately 0.25 to 4 times the 400 mg clinical dose based on body surface area [BSA] comparison), and abortions occurred at 75 mg/kg (approximately 4 times the 400 mg clinical dose based on BSA); no adverse fetal effects were observed.

In several studies in which pregnant rats received fluconazole orally during organogenesis, maternal weight gain was impaired and placental weights were increased at 25 mg/kg. There were no fetal effects at 5 mg/kg or 10 mg/kg; increases in fetal anatomical variants (supernumerary ribs, renal pelvis dilation) and delays in ossification were observed at 25 mg/kg and 50 mg/kg and higher doses. At doses ranging from 80 to 320 mg/kg (approximately 2 to 8 times the 400 mg clinical dose based on BSA), embryolethality in rats was increased and fetal abnormalities included wavy ribs, cleft palate, and abnormal craniofacial ossification. These effects are consistent with the inhibition of estrogen synthesis in rats and may be a result of known effects of lowered estrogen on pregnancy, organogenesis, and parturition.

Nursing Mothers

Fluconazole was present in low levels in breast milk following administration of a single 150 mg dose, based on data from a study in 10 breastfeeding women who temporarily or permanently discontinued breastfeeding 5 days to 19 months postpartum. The estimated daily infant dose of fluconazole from breast milk (assuming mean milk consumption of 150 mL/kg/day) based on the mean peak milk concentration (2.61 mcg/mL [range: 1.57 to 3.65 mcg/mL] at 5.2 hours post-dose) was 0.39 mg/kg/day, which is approximately 13% of the recommended pediatric dose for oropharyngeal candidiasis. (Labeled pediatric dose is 6 mg/kg/day on the first day followed by 3 mg/kg/day; estimated infant dose is 13% of 3 mg/kg/day maintenance dose). There are no data on fluconazole levels in milk after repeated use or after high-dose fluconazole. A published survey of 96 breastfeeding women who were treated with fluconazole 150 mg every other day (average of 7.3 capsules [range 1 to 29 capsules]) for lactation-associated candida of the breasts reported no serious adverse reactions in infants. Caution should be exercised when DIFLUCAN is administered to a nursing woman.

Pediatric Use

Use in Pediatric Patients for the Treatment of Oropharyngeal Candidiasis

An open-label, randomized, controlled trial has shown DIFLUCAN to be effective in the treatment of oropharyngeal candidiasis in pediatric patients 6 months to 13 years of age. (See CLINICAL STUDIES.)

Use in Pediatric Patients for the Treatment of Candida Esophagitis, Systemic Candida Infections, or Cryptococcal Meningitis:

The use of DIFLUCAN in pediatric patients with cryptococcal meningitis, Canida esophagitis, or systemic Candida infections is supported by the efficacy shown for these indications in adults and by the results from several small noncomparative pediatric clinical studies. In addition, pharmacokinetic studies in pediatric patients (See CLINICAL PHARMACOLOGY) have established a dose proportionality between pediatric patients and adults. (See DOSAGE AND ADMINISTRATION.)

In a noncomparative study of DIFLUCAN administered to pediatric patients (from birth to less than 17 years) with serious systemic fungal infections, most of which were candidemia, the effectiveness of DIFLUCAN was similar to that reported for the treatment of candidemia in adults. Of 17 subjects with culture-confirmed candidemia, 11 of 14 (79%) with baseline symptoms (3 were asymptomatic) had a clinical cure; 13/15 (87%) of evaluable patients had a mycologic cure at the end of treatment but two of these patients relapsed at 10 and 18 days, respectively, following cessation of therapy.

The efficacy of DIFLUCAN for the suppression of cryptococcal meningitis was successful in 4 of 5 pediatric patients (4 years to 10 years of age) treated in a compassionate-use study of fluconazole for the treatment of life‑threatening or serious mycosis.

There are limited clinical data to support the efficacy of DIFLUCAN for the primary treatment of cryptococcal meningitis in pediatric patients.

The safety profile of DIFLUCAN has been studied in 577 pediatric patients from 1 day to 17 years of age who received doses ranging from 1 to 15 mg/kg/day for 1 to 1,616 days. (See ADVERSE REACTIONS.)

Use in Pediatric Patients on Extracorporeal Membrane Oxygenation (ECMO)

A prospective, open-label, single-center study was conducted to determine the PK and safety of fluconazole in pediatric patients (ages: from birth to 17 years of age) on ECMO (see CLINICAL PHARMACOLOGY). A loading dose of 35-mg/kg is recommended in pediatric patients on ECMO due to increased volume of distribution (see DOSAGE AND ADMINISTRATION).

Use in Prophylaxis of Invasive Candida Infections in Pediatric Patients (premature infants weighing less than 750 grams at birth)

Safety and effectiveness of DIFLUCAN for the prophylaxis of invasive candidiasis in pediatric patients (premature infants weighing less than 750 grams at birth) have not been established.

A prospective, randomized, double-blind, placebo-controlled, multicenter trial was conducted in premature infants weighing less than 750 grams at birth to evaluate the efficacy and safety of prophylactic DIFLUCAN 6-mg/kg administered twice weekly for 6 weeks versus placebo (NCT00734539). Efficacy was assessed using the endpoint of death or candidiasis by study day 49. The results are summarized in Table 4.

Table 4: Death or Candidiasis by Day 49 in Premature Infants Receiving DIFLUCAN Prophylaxis

 | DIFLUCAN; (N=188); n (%) | Placebo; (N=173); n (%) | P-value | Difference (95% CI)
Death or candidiasis* | 33 (17.6) | 38 (22.0) | 0.2954 | -4.4(-12.6, 3.8)
Components of endpoint**; Death; Candidiasis; Missing | 27 (14.4); 6 (3.2); 2 (1.0) | 25 (14.5); 16 (9.2); 1 (0.5)

* Subjects with missing data are imputed as having candidiasis or died.

**Subjects may be counted more than once as two fluconazole subjects and four placebo subjects diagnosed with candidiasis subsequently died by day 49.

The most common fatal serious adverse reactions in the DIFLUCAN vs placebo arms, respectively, were necrotizing enterocolitis (NEC), 9 (5%) vs 9 (5%); neonatal bacterial sepsis, 6 (3%) vs 7 (4%); and neonatal respiratory failure, 4 (2%) vs 2 (0.6%).

The most common serious adverse reactions (>5%), reported in patients receiving DIFLUCAN prophylaxis are displayed in Table 5.

Table 5. Serious Adverse Reactions* Occurring in >5% of Infants Receiving DIFLUCAN Prophylaxis

Adverse Reaction | DIFLUCAN; (N=188); n(%) | Placebo; (N=173); n (%)
Necrotizing Enterocolitis (NEC) | 27 (14) | 28 (16)
Intestinal Perforation (includes ileal/small intestinal perforation) | 13 (7) | 7 (4)
Neonatal Respiratory Arrest/Neonatal Respiratory Failure | 13 (7) | 4 (2)
Bacterial Sepsis, Neonatal | 10 (5) | 12 (7)

*All serious adverse reactions were assessed and recorded up through 30 days after the final dose of study drug. Serious adverse reactions included both fatal and non-fatal outcomes.

Geriatric Use

In non-AIDS patients, side effects possibly related to fluconazole treatment were reported in fewer patients aged 65 and older (9%, n =339) than for younger patients (14%, n=2240). However, there was no consistent difference between the older and younger patients with respect to individual side effects. Of the most frequently reported (>1%) side effects, rash, vomiting, and diarrhea occurred in greater proportions of older patients. Similar proportions of older patients (2.4%) and younger patients (1.5%) discontinued fluconazole therapy because of side effects. In post-marketing experience, spontaneous reports of anemia and acute renal failure were more frequent among patients 65 years of age or older than in those between 12 and 65 years of age. Because of the voluntary nature of the reports and the natural increase in the incidence of anemia and renal failure in the elderly, it is however not possible to establish a causal relationship to drug exposure.

Controlled clinical trials of fluconazole did not include sufficient numbers of patients aged 65 and older to evaluate whether they respond differently from younger patients in each indication. Other reported clinical experience has not identified differences in responses between the elderly and younger patients.

Fluconazole is primarily cleared by renal excretion as unchanged drug. Because elderly patients are more likely to have decreased renal function, care should be taken to adjust dose based on creatinine clearance. It may be useful to monitor renal function. (See CLINICAL PHARMACOLOGY and DOSAGE AND ADMINISTRATION.)

ADVERSE REACTIONS

DIFLUCAN is generally well tolerated.

In some patients, particularly those with serious underlying diseases such as AIDS and cancer, changes in renal and hematological function test results and hepatic abnormalities have been observed during treatment with fluconazole and comparative agents, but the clinical significance and relationship to treatment is uncertain.

In Patients Receiving a Single Dose for Vaginal Candidiasis:

During comparative clinical studies conducted in the United States, 448 patients with vaginal candidiasis were treated with DIFLUCAN, 150 mg single dose. The overall incidence of side effects possibly related to DIFLUCAN was 26%. In 422 patients receiving active comparative agents, the incidence was 16%. The most common treatment-related adverse events reported in the patients who received 150 mg single dose fluconazole for vaginitis were headache (13%), nausea (7%), and abdominal pain (6%). Other side effects reported with an incidence equal to or greater than 1% included diarrhea (3%), dyspepsia (1%), dizziness (1%), and taste perversion (1%). Most of the reported side effects were mild to moderate in severity. Rarely, angioedema and anaphylactic reaction have been reported in marketing experience.

In Patients Receiving Multiple Doses for Other Infections:

Sixteen percent of over 4000 patients treated with DIFLUCAN (fluconazole) in clinical trials of 7 days or more experienced adverse events. Treatment was discontinued in 1.5% of patients due to adverse clinical events and in 1.3% of patients due to laboratory test abnormalities.

Clinical adverse events were reported more frequently in HIV infected patients (21%) than in non-HIV infected patients (13%); however, the patterns in HIV infected and non-HIV infected patients were similar. The proportions of patients discontinuing therapy due to clinical adverse events were similar in the two groups (1.5%).

The following treatment-related clinical adverse events occurred at an incidence of 1% or greater in 4048 patients receiving DIFLUCAN for 7 or more days in clinical trials: nausea 3.7%, headache 1.9%, skin rash 1.8%, vomiting 1.7%, abdominal pain 1.7%, and diarrhea 1.5%.

Hepato-biliary:

In combined clinical trials and marketing experience, there have been rare cases of serious hepatic reactions during treatment with DIFLUCAN. (See WARNINGS.) The spectrum of these hepatic reactions has ranged from mild transient elevations in transaminases to clinical hepatitis, cholestasis and fulminant hepatic failure, including fatalities. Instances of fatal hepatic reactions were noted to occur primarily in patients with serious underlying medical conditions (predominantly AIDS or malignancy) and often while taking multiple concomitant medications. Transient hepatic reactions, including hepatitis and jaundice, have occurred among patients with no other identifiable risk factors. In each of these cases, liver function returned to baseline on discontinuation of DIFLUCAN.

In two comparative trials evaluating the efficacy of DIFLUCAN for the suppression of relapse of cryptococcal meningitis, a statistically significant increase was observed in median AST (SGOT) levels from a baseline value of 30 IU/L to 41 IU/L in one trial and 34 IU/L to 66 IU/L in the other. The overall rate of serum transaminase elevations of more than 8 times the upper limit of normal was approximately 1% in fluconazole-treated patients in clinical trials. These elevations occurred in patients with severe underlying disease, predominantly AIDS or malignancies, most of whom were receiving multiple concomitant medications, including many known to be hepatotoxic. The incidence of abnormally elevated serum transaminases was greater in patients taking DIFLUCAN concomitantly with one or more of the following medications: rifampin, phenytoin, isoniazid, valproic acid, or oral sulfonylurea hypoglycemic agents.

Post-Marketing Experience

In addition, the following adverse events have occurred during post-marketing experience.

Immunologic: In rare cases, anaphylaxis (including angioedema, face edema and pruritus) has been reported.

Body as a Whole: Asthenia, fatigue, fever, malaise.

Cardiovascular: QT prolongation, torsade de pointes. (See PRECAUTIONS.)

Central Nervous System: Seizures, dizziness.

Hematopoietic and Lymphatic: Leukopenia, including neutropenia and agranulocytosis, thrombocytopenia.

Metabolic: Hypercholesterolemia, hypertriglyceridemia, hypokalemia.

Gastrointestinal: Cholestasis, dry mouth, hepatocellular damage, dyspepsia, vomiting.

Other Senses: Taste perversion.

Musculoskeletal System: myalgia.

Nervous System: Insomnia, paresthesia, somnolence, tremor, vertigo.

Skin and Appendages: Acute generalized exanthematous pustulosis, drug eruption including fixed drug eruption, increased sweating, exfoliative skin disorders including Stevens-Johnson syndrome and toxic epidermal necrolysis, drug reaction with eosinophilia and systemic symptoms (DRESS) (See WARNINGS), alopecia.

Adverse Reactions in Pediatric Patients:

The pattern and incidence of adverse events and laboratory abnormalities recorded during pediatric clinical trials are comparable to those seen in adults.

In Phase II/III clinical trials conducted in the United States and in Europe, 577 pediatric patients, ages 1 day to 17 years were treated with DIFLUCAN at doses up to 15 mg/kg/day for up to 1,616 days. Thirteen percent of pediatric patients experienced treatment-related adverse events. The most commonly reported events were vomiting (5%), abdominal pain (3%), nausea (2%), and diarrhea (2%). Treatment was discontinued in 2.3% of patients due to adverse clinical events and in 1.4% of patients due to laboratory test abnormalities. The majority of treatment-related laboratory abnormalities were elevations of transaminases or alkaline phosphatase.

Percentage of Patients With Treatment-Related Side Effects
 | Fluconazole (N=577) | Comparative Agents (N=451)
With any side effect | 13.0 | 9.3
Vomiting | 5.4 | 5.1
Abdominal pain | 2.8 | 1.6
Nausea | 2.3 | 1.6
Diarrhea | 2.1 | 2.2

Clinical Trials Experience in Pediatric Patients

Safety in Prophylaxis of Invasive Candida Infections in Premature infants weighing less than 750 grams at birth

In a Phase 3 clinical trial of pediatric patients (premature infants weighing less than 750 grams at birth), the incidence of intestinal perforation in infants receiving DIFLUCAN prophylaxis was higher compared to infants receiving placebo (see PRECAUTIONS: Pediatric Use).

Safety in Pediatric Patients Receiving ECMO

A cohort of 20 pediatric patients (1 day to 17 years of age) on ECMO received DIFLUCAN in a prospective, open-label, single-center safety and PK ECMO study. The adverse reaction profile of DIFLUCAN in these patients was similar to that of adult and pediatric non-ECMO patients (See PRECAUTIONS: Pediatric Use).

OVERDOSAGE

There have been reports of overdose with fluconazole accompanied by hallucination and paranoid behavior.

In the event of overdose, symptomatic treatment (with supportive measures and gastric lavage if clinically indicated) should be instituted.

Fluconazole is largely excreted in urine. A 3-hour hemodialysis session decreases plasma levels by approximately 50%.

In mice and rats receiving very high doses of fluconazole, clinical effects in both species included decreased motility and respiration, ptosis, lacrimation, salivation, urinary incontinence, loss of righting reflex, and cyanosis; death was sometimes preceded by clonic convulsions.

DOSAGE AND ADMINISTRATION

Dosage and Administration in Adults:

Single Dose

Vaginal candidiasis:

The recommended dosage of DIFLUCAN for vaginal candidiasis is 150 mg as a single oral dose.

Multiple Dose

SINCE ORAL ABSORPTION IS RAPID AND ALMOST COMPLETE, THE DAILY DOSE OF DIFLUCAN (FLUCONAZOLE) IS THE SAME FOR ORAL (TABLETS AND SUSPENSION) AND INTRAVENOUS ADMINISTRATION. In general, a loading dose of twice the daily dose is recommended on the first day of therapy to result in plasma concentrations close to steady-state by the second day of therapy.

The daily dose of DIFLUCAN for the treatment of infections other than vaginal candidiasis should be based on the infecting organism and the patient's response to therapy. Treatment should be continued until clinical parameters or laboratory tests indicate that active fungal infection has subsided. An inadequate period of treatment may lead to recurrence of active infection. Patients with AIDS and cryptococcal meningitis or recurrent oropharyngeal candidiasis usually require maintenance therapy to prevent relapse.

Oropharyngeal candidiasis:

The recommended dosage of DIFLUCAN for oropharyngeal candidiasis is 200 mg on the first day, followed by 100 mg once daily. Clinical evidence of oropharyngeal candidiasis generally resolves within several days, but treatment should be continued for at least 2 weeks to decrease the likelihood of relapse.

Esophageal candidiasis:

The recommended dosage of DIFLUCAN for esophageal candidiasis is 200 mg on the first day, followed by 100 mg once daily. Doses up to 400 mg/day may be used, based on medical judgment of the patient's response to therapy. Patients with esophageal candidiasis should be treated for a minimum of three weeks and for at least two weeks following resolution of symptoms.

Systemic Candida infections:

For systemic Candida infections including candidemia, disseminated candidiasis, and pneumonia, optimal therapeutic dosage and duration of therapy have not been established. In open, noncomparative studies of small numbers of patients, doses of up to 400 mg daily have been used.

Urinary tract infections and peritonitis:

For the treatment of Candida urinary tract infections and peritonitis, daily doses of 50 to 200 mg have been used in open, noncomparative studies of small numbers of patients.

Cryptococcal meningitis:

The recommended dosage for treatment of acute cryptococcal meningitis is 400 mg on the first day, followed by 200 mg once daily. A dosage of 400 mg once daily may be used, based on medical judgment of the patient's response to therapy. The recommended duration of treatment for initial therapy of cryptococcal meningitis is 10 to 12 weeks after the cerebrospinal fluid becomes culture negative. The recommended dosage of DIFLUCAN for suppression of relapse of cryptococcal meningitis in patients with AIDS is 200 mg once daily.

Prophylaxis in patients undergoing bone marrow transplantation:

The recommended DIFLUCAN daily dosage for the prevention of candidiasis in patients undergoing bone marrow transplantation is 400 mg, once daily. Patients who are anticipated to have severe granulocytopenia (less than 500 neutrophils cells/mm^3) should start DIFLUCAN prophylaxis several days before the anticipated onset of neutropenia, and continue for 7 days after the neutrophil count rises above 1000 cells/mm^3.

Dosage and Administration in Pediatric Patients

Oropharyngeal candidiasis:

The recommended dosage of DIFLUCAN for oropharyngeal candidiasis in pediatric patients 6 months and older is 6 mg/kg on the first day, followed by 3 mg/kg once daily. Treatment should be administered for at least 2 weeks to decrease the likelihood of relapse.

Esophageal candidiasis:

For the treatment of esophageal candidiasis, the recommended dosage of DIFLUCAN in pediatric patients 6 months and older is 6 mg/kg on the first day, followed by 3 mg/kg once daily. Doses up to 12 mg/kg/day may be used, based on medical judgment of the patient’s response to therapy. Patients with esophageal candidiasis should be treated for a minimum of three weeks and for at least 2 weeks following the resolution of symptoms.

Systemic Candida infections:

The following dosing regimens in Table 6 are recommended for pediatric patients to achieve systemic exposures similar to adults for the treatment of systemic Candida infections, i.e., to maintain an AUC0-24 between 400-800 mg*h/L.

Table 6: Recommended Dosing Regimens for the Treatment of Systemic Candida Infections in Pediatric Patients

Patient age | Dosing regimen
3 months and older | A loading dose of 25-mg/kg on the first day (not to exceed 800 mg) followed by 12-mg/kg once daily (not to exceed 400 mg).
Birth to 3 months postnatal age and gestational age 30 weeks and above | 25-mg/kg on the first day, followed by 12-mg/kg once daily
Birth to 3 months postnatal age and gestational age less than 30 weeks | 25-mg/kg on the first day, followed by 9-mg/kg once daily

Patients with systemic candidiasis should be treated for a minimum of 3 weeks and for at least 2 weeks following the resolution of symptoms.

Dosing in Pediatric Patients on ECMO:

The recommended dosage of DIFLUCAN in pediatric patients 3 months and older on ECMO is 35-mg/kg on the first day (not to exceed 800 mg) followed by 12-mg/kg once daily (not to exceed 400 mg).

For patients from birth to 3 months postnatal age, and gestational age less than 30 weeks, a loading dose of 35-mg/kg on the first day followed by 9-mg/kg once daily is recommended. For patients from birth to 3 months postnatal age and gestational age 30 weeks and above, a loading dose of 35-mg/kg on the first day followed by 12-mg/kg once daily is recommended.

Cryptococcal meningitis:

For the treatment of acute cryptococcal meningitis, the recommended dosage is 12 mg/kg on the first day, followed by 6 mg/kg once daily. A dosage of 12 mg/kg once daily may be used, based on medical judgment of the patient's response to therapy. The recommended duration of treatment for initial therapy of cryptococcal meningitis is 10 to 12 weeks after the cerebrospinal fluid becomes culture negative. For suppression of relapse of cryptococcal meningitis in pediatric patients with AIDS, the recommended dose of DIFLUCAN is 6 mg/kg once daily.

Dosage In Patients With Impaired Renal Function:

Fluconazole is cleared primarily by renal excretion as unchanged drug. There is no need to adjust single dose therapy for vaginal candidiasis because of impaired renal function. In patients with impaired renal function who will receive multiple doses of DIFLUCAN, an initial loading dose of 50 mg to 400 mg should be given. After the loading dose, the daily dose (according to indication) should be based on the following summary:

Creatinine Clearance (mL/min) | Recommended Dose (%)
>50 | 100
≤50 (no dialysis) | 50
Hemodialysis | 100% after each hemodialysis

Patients on hemodialysis should receive 100% of the recommended dose after each hemodialysis; on non-dialysis days, patients should receive a reduced dose according to their creatinine clearance.

These are suggested dose adjustments based on pharmacokinetics following administration of multiple doses. Further adjustment may be needed depending upon clinical condition.

When serum creatinine is the only measure of renal function available, the following formula (based on sex, weight, and age of the patient) should be used to estimate the creatinine clearance in adults:

Males:

Weight (kg) × (140 – age)

72 × serum creatinine (mg/100 mL)

Females: 0.85 × above value

Although the pharmacokinetics of fluconazole has not been studied in pediatric patients with renal insufficiency, dosage reduction in pediatric patients with renal insufficiency should parallel that recommended for adults. The following formula may be used to estimate creatinine clearance in pediatric patients:

K × | linear length or height (cm)
 | serum creatinine (mg/100 mL)

(Where K=0.55 for pediatric patients older than 1 year and 0.45 for infants.)

Administration

DIFLUCAN is administered orally. DIFLUCAN can be taken with or without food.

Directions for Mixing the Oral Suspension

Prepare a suspension at time of dispensing as follows: tap bottle until all the powder flows freely. To reconstitute, add 24 mL of distilled water or Purified Water (USP) to fluconazole bottle and shake vigorously to suspend powder. Each bottle will deliver 35 mL of suspension. The concentrations of the reconstituted suspensions are as follows:

Fluconazole Content per Bottle | Concentration of Reconstituted Suspension
350 mg | 10 mg/mL
1400 mg | 40 mg/mL

Note: Shake oral suspension well before using. Store reconstituted suspension between 30°C (86°F) and 5°C (41°F) and discard unused portion after 2 weeks. Protect from freezing.

HOW SUPPLIED

DIFLUCAN Tablets: Pink trapezoidal tablets containing 50, 100, or 200 mg of fluconazole are packaged in bottles or unit dose blisters. The 150 mg fluconazole tablets are pink and oval shaped, packaged in a single dose unit blister.

DIFLUCAN Tablets are supplied as follows:

DIFLUCAN 50 mg Tablets: Engraved with "DIFLUCAN" and "50" on the front and "ROERIG" on the back.

 | NDC 0049-3410-30 | Bottles of 30

DIFLUCAN 100 mg Tablets: Engraved with "DIFLUCAN" and "100" on the front and "ROERIG" on the back.

 | NDC 0049-3420-30 | Bottles of 30
 | NDC 0049-3420-41 | Unit dose package of 100

DIFLUCAN 150 mg Tablets: Engraved with "DIFLUCAN" and "150" on the front and "ROERIG" on the back.

 | NDC 0049-3500-79 | Unit dose package of 1

DIFLUCAN 200 mg Tablets: Engraved with "DIFLUCAN" and "200" on the front and "ROERIG" on the back.

 | NDC 0049-3430-30 | Bottles of 30
 | NDC 0049-3430-41 | Unit dose package of 100

Storage

Store tablets below 30°C (86°F).

DIFLUCAN for Oral Suspension: DIFLUCAN for Oral Suspension is supplied as an orange-flavored powder to provide 35 mL per bottle as follows:

 | NDC 0049-3440-19 | Fluconazole 350 mg per bottle
 | NDC 0049-3450-19 | Fluconazole 1400 mg per bottle

Storage:

Store dry powder below 30°C (86°F). Store reconstituted suspension between 30°C (86°F) and 5°C (41°F) and discard unused portion after 2 weeks. Protect from freezing.

LAB-0099-33.0
Revised: 3/2025

PATIENT INFORMATION
DIFLUCAN® (dye-FLEW-kan)
(fluconazole)
Tablets

This leaflet contains important information about DIFLUCAN. It is not meant to take the place of your healthcare provider's instructions. Read this information carefully before you take DIFLUCAN. Ask your healthcare provider if you do not understand any of this information or if you want to know more about DIFLUCAN.

What is DIFLUCAN?
DIFLUCAN is a prescription medicine used to treat vaginal yeast infections caused by a yeast called Candida. DIFLUCAN helps stop too much yeast from growing in the vagina so the yeast infection goes away.
DIFLUCAN is different from other treatments for vaginal yeast infections because it is a tablet taken by mouth. DIFLUCAN is also used for other conditions. However, this leaflet is only about using DIFLUCAN for vaginal yeast infections. For information about using DIFLUCAN for other reasons, ask your healthcare provider. See the section of this leaflet for information about vaginal yeast infections.

What is a vaginal yeast infection?
It is normal for a certain amount of yeast to be found in the vagina. Sometimes too much yeast starts to grow in the vagina and this can cause a yeast infection. Vaginal yeast infections are common. About three out of every four adult women will have at least one vaginal yeast infection during their life.
Some medicines and medical conditions can increase your chance of getting a yeast infection. If you are pregnant, have diabetes, use birth control pills, or take antibiotics you may get yeast infections more often than other women. Personal hygiene and certain types of clothing may increase your chances of getting a yeast infection. Ask your healthcare provider for tips on what you can do to help prevent vaginal yeast infections.
If you get a vaginal yeast infection, you may have any of the following symptoms:

- itching
- a burning feeling when you urinate
- redness
- soreness
- a thick white vaginal discharge that looks like cottage cheese

Do not take DIFLUCAN if you.

- take the following medicines:
  - quinidine
  - erythromycin
  - pimozide
  - are allergic to fluconazole, the active ingredient in DIFLUCAN, or any of the ingredients in DIFLUCAN. See the end of this Patient Information leaflet for a complete list of ingredients in DIFLUCAN.

Before you take DIFLUCAN, tell your healthcare provider about all of your medical conditions, if you:

- have liver problems
- have kidney problems
- have heart problems including heart arrythmias
- have hypokalemia (low potassium)
- are pregnant or plan to become pregnant. Tell your healthcare provider right away if you become pregnant while taking DIFLUCAN. You and your healthcare provider will decide if DIFLUCAN is right for you. If you may become pregnant you should use a birth-control (contraceptive) method while taking DIFLUCAN and for 1 week after your final dose.
- are breastfeeding or plan to breastfeed. DIFLUCAN can pass into your breastmilk. Talk to your healthcare provider about the best way to feed your baby while you are taking DIFLUCAN.

Before you start taking DIFLUCAN, tell your healthcare provider about all the medicines you take, including prescription and over-the-counter medicines, vitamins, and herbal supplements. Especially tell your healthcare provider if you take:

- diabetes medicines such as glyburide, tolbutamide, glipizide
- blood pressure medicines like hydrochlorothiazide, losartan, amlodipine, verapamil, nifedipine or felodipine
- blood thinners such as warfarin
- cyclosporine, tacrolimus or sirolimus (used to prevent rejection of organ transplants)
- rifampin or rifabutin for tuberculosis
- phenytoin or carbamazepine to control seizures
- theophylline to control asthma
- quinidine (used to correct disturbances in heart rhythm)
- amiodarone (used for treating uneven heartbeats 'arrhythmias')
- amitriptyline or nortriptyline for depression
- pimozide for psychiatric illness
- amphotericin B or voriconazole for fungal infections
- erythromycin for bacterial infections
- olaparib, cyclophosphamide or vinca alkaloids such as vincristine or vinblastine for treatment of cancer
- fentanyl, alfentanil or methadone for chronic pain
- ibrutinib used for treating blood cancer
- ivacaftor or ivacaftor combinations, such as tezacaftor/ivacaftor and ivacaftor/tezacaftor/elexacaftor, used to treat cystic fibrosis
- lurasidone used to treat schizophrenia or depression
- lemborexant, used for the treatment of insomnia
- lipid lowering drugs such as atorvastatin, simvastatin, and fluvastatin
- non-steroidal anti-inflammatory drugs including celecoxib, ibuprofen, and naproxen
- prednisone, a steroid used to treat skin, gastrointestinal, hematological or respiratory disorders
- antiviral medications used to treat HIV like saquinavir or zidovudine
- tofacitinib for rheumatoid arthritis
- abrocitinib (used to treat atopic dermatitis, also known as eczema)
- vitamin A nutritional supplement
- tolvaptan used to treat hyponatremia (low levels of sodium in your blood) or to slow kidney function decline

Since there are many brand names for these medicines, check with your healthcare provider or pharmacist if you have any questions.

How should I take DIFLUCAN?

- Take DIFLUCAN exactly as your healthcare provider tells you to.
- Take DIFLUCAN by mouth with or without food.
- If you take too much DIFLUCAN, call your healthcare provider or go to the nearest emergency room right away.

What should I avoid while taking DIFLUCAN?
DIFLUCAN can cause dizziness and seizures. Do not drive or operate machinery until you know how DIFLUCAN affects you.

What are the possible side effects of DIFLUCAN?
DIFLUCAN may cause serious side effects including:

- serious liver problems. Some people with serious medical problems have developed serious liver problems that became life-threatening or caused death while taking DIFLUCAN. Sometimes these liver problems can be reversed when you stop taking DIFLUCAN. Tell your healthcare provider right away if you have symptoms of serious liver problems including:

- dark colored urine
- severe skin itching
- yellowing of the skin and eyes (jaundice)

- light-colored stools
- tiredness

- vomiting
- loss of appetite

- serious allergic reactions: Serious allergic reactions (anaphylaxis) have happened while taking DIFLUCAN. Stop taking DIFLUCAN, call your healthcare provider or go to the nearest hospital emergency room right away if you get any signs or symptoms of an allergic reaction including:

- shortness of breath
- fever
- swelling of the eyelids

- coughing
- skin rash, hives, blisters or skin peeling
- face, mouth, neck, or any other part of the body

- wheezing
- throbbing of the heart or ears
- chills

- serious skin problems. Some people with serious medical problems have developed serious skin problems that have caused death while taking DIFLUCAN. Tell your healthcare provider right away if you develop a rash while taking DIFLUCAN.

The most common side effects of DIFLUCAN include:

- headache
- dizziness

- diarrhea
- stomach pain

- nausea or upset stomach
- changes in the way food tastes

Other side effects include:

- adrenal insufficiency: Some people who have taken DIFLUCAN developed adrenal insufficiency that was reversible. Tell your healthcare provider right away if you have symptoms of adrenal insufficiency including:

- long lasting fatigue

- muscle weakness

- loss of appetite

- weight loss

- stomach pain

- dizziness

- nausea

- vomiting

- dizziness or seizures.

These are not all the possible side effects of DIFLUCAN.
Call your healthcare provider for medical advice about side effects. You may report side effects to FDA at 1-800-FDA-1088.

How should I store DIFLUCAN?
Store DIFLUCAN tablets below 86°F (30°C).
Keep DIFLUCAN and all medicines out of the reach of children.

General information about the safe and effective use of DIFLUCAN.
Medicines are sometimes prescribed for purposes other than those listed in a Patient Information leaflet. Do not use DIFLUCAN for a condition for which it was not prescribed. Do not give DIFLUCAN to other people, even if they have the same symptoms you have. It may harm them.
You can ask your healthcare provider for information about DIFLUCAN that is written for health professionals.

What are the ingredients in DIFLUCAN?
Active ingredient: fluconazole
Inactive ingredients: microcrystalline cellulose, dibasic calcium phosphate anhydrous, povidone, croscarmellose sodium, FD&C Red No. 40 aluminum lake dye, and magnesium stearate.

For Medical Information about DIFLUCAN, please visit www.pfizermedinfo.com or call 1-800-438-1985.

This Patient Information has been approved by the U.S. Food and Drug Administration

Revised: 3/2025

LAB-0380-16.0

PRINCIPAL DISPLAY PANEL - 50 mg Tablet Bottle Label

Pfizer

NDC 0049-3410-30

DIFLUCAN®
(Fluconazole Tablets)

50 mg

30 Tablets
Rx only

PRINCIPAL DISPLAY PANEL - 100 mg Tablet Bottle Label

Pfizer

NDC 0049-3420-30

DIFLUCAN®
(Fluconazole Tablets)

100 mg

30 Tablets
Rx only

PRINCIPAL DISPLAY PANEL - 100 mg Tablet Blister Pack

DIFLUCAN®
(Fluconazole Tablet)

100 mg

Distributed by
ROERIG
DIV OF PFIZER INC, NY, NY 10017
MADE IN USA (includes foreign content)

13041200

EXP & LOT AREA

PRINCIPAL DISPLAY PANEL - 100 mg Tablet Blister Pack Carton

UNIT DOSE

Pfizer

NDC 0049-3420-41

DIFLUCAN®
(Fluconazole Tablets)

100 mg

For in-institution use only

100 Tablets
Rx only

PRINCIPAL DISPLAY PANEL - 150 mg Tablet Blister Pack

NDC 0049-3500-79

1 Blister x 1 Tablet

Pfizer

Diflucan®
(fluconazole tablet)
150 mg

Directions:
Push tablet through
foil and take by mouth

Warning: Do not use if you are pregnant, think you may

be pregnant or are trying to become pregnant unless

directed by your physician. If you become pregnant after

taking this medicine, contact your physician.

You should consider using a reliable means of

contraception for approximately 1 week after the dose.

Rx only

PRINCIPAL DISPLAY PANEL - 12 x 150 mg Tablet Blister Pack Carton

Pfizer

NDC 0049-3500-79

Diflucan®
(fluconazole tablet)
150 mg

12 Blisters x 1 Tablet
Rx only

PRINCIPAL DISPLAY PANEL - 200 mg Tablet Bottle Label

Pfizer

NDC 0049-3430-30

DIFLUCAN®
(Fluconazole Tablets)

200 mg

30 Tablets
Rx only

PRINCIPAL DISPLAY PANEL - 200 mg Tablet Blister Pack

DIFLUCAN®
(Fluconazole Tablet)

200 mg

Distributed by
ROERIG
DIV OF PFIZER INC, NY, NY 10017
MADE IN USA (includes foreign content)

13041700

EXP & LOT AREA

PRINCIPAL DISPLAY PANEL - 200 mg Tablet Blister Pack Carton

UNIT DOSE

Pfizer

NDC 0049-3430-41

DIFLUCAN®
(Fluconazole Tablets)

200 mg

For in-institution use only

100 Tablets
Rx only

PRINCIPAL DISPLAY PANEL - 10 mg/mL Bottle Label

Pfizer

NDC 0049-3440-19

DIFLUCAN®
(fluconazole) for Oral
Suspension

10 mg/mL

ORANGE FLAVORED
35 mL when reconstituted

Rx only

PRINCIPAL DISPLAY PANEL - 10 mg/mL Bottle Carton

Pfizer

NDC 0049-3440-19

DIFLUCAN®
(fluconazole) for Oral
Suspension

10 mg/mL

ORANGE FLAVORED

35 mL when reconstituted

Rx only

PRINCIPAL DISPLAY PANEL - 40 mg/mL Bottle Label

Pfizer

NDC 0049-3450-19

DIFLUCAN®
(fluconazole) for Oral
Suspension

40 mg/mL

ORANGE FLAVORED
35 mL when reconstituted

Rx only

PRINCIPAL DISPLAY PANEL - 40 mg/mL Bottle Carton

Pfizer

NDC 0049-3450-19

DIFLUCAN®
(fluconazole) for Oral
Suspension

40 mg/mL

ORANGE FLAVORED

35 mL when reconstituted

Rx only